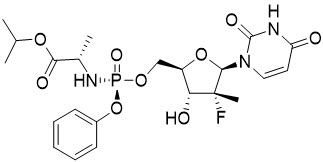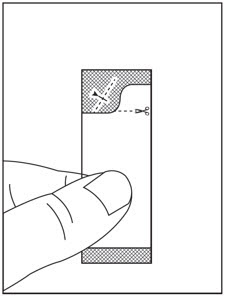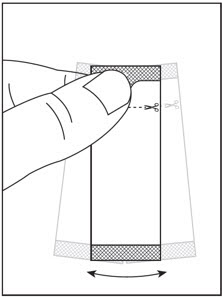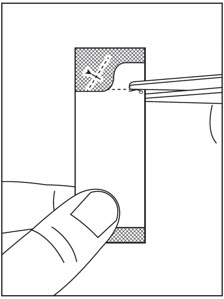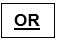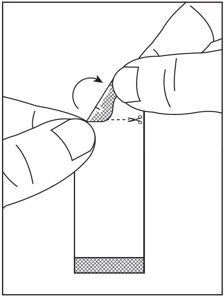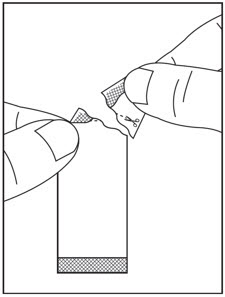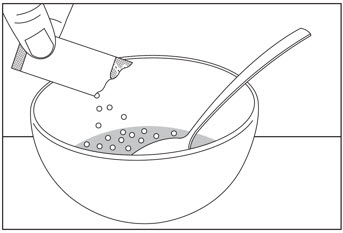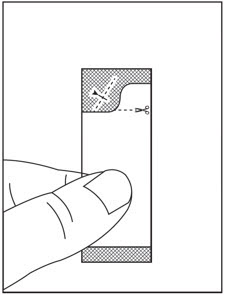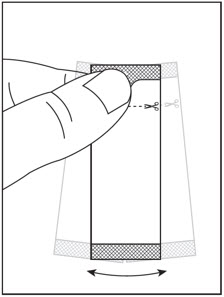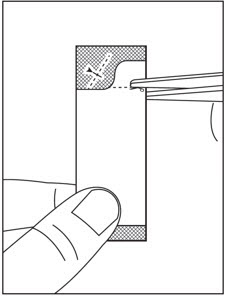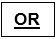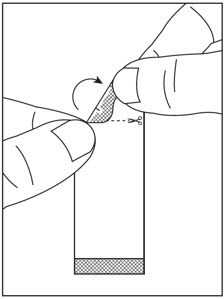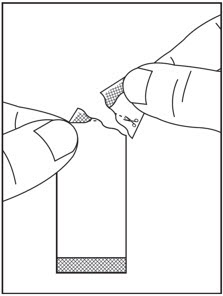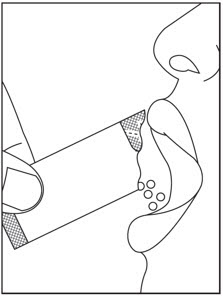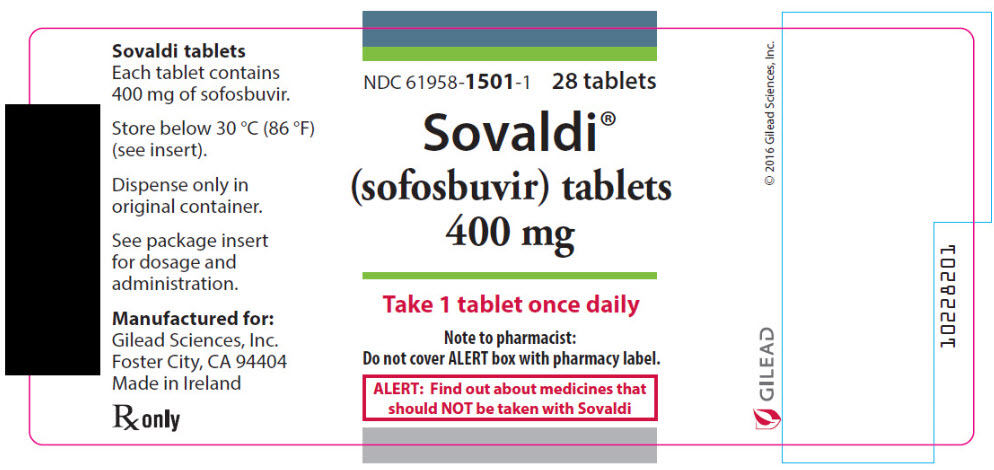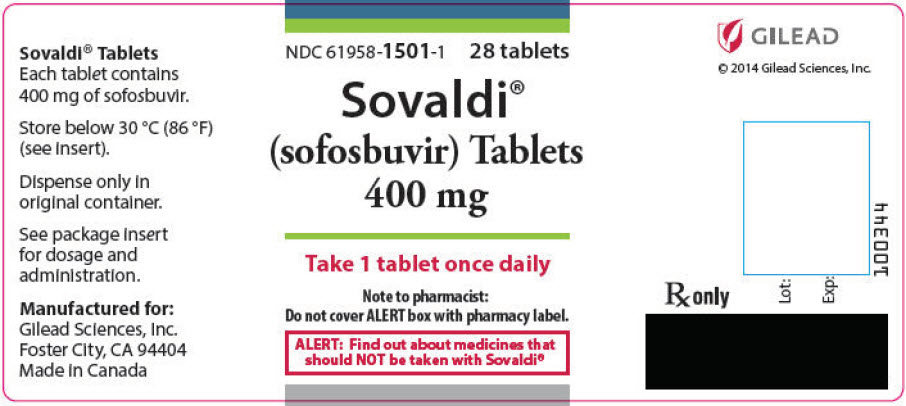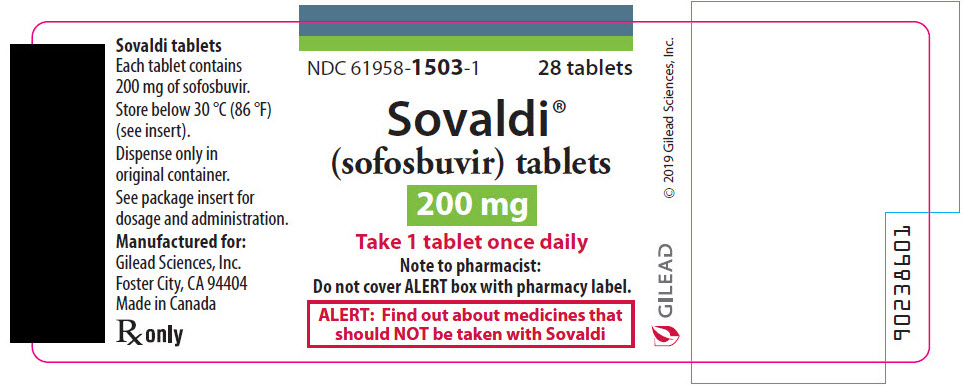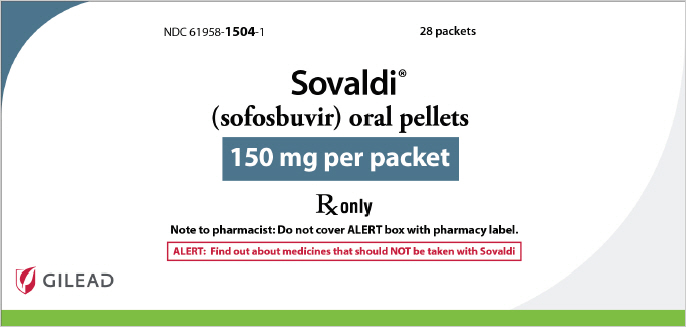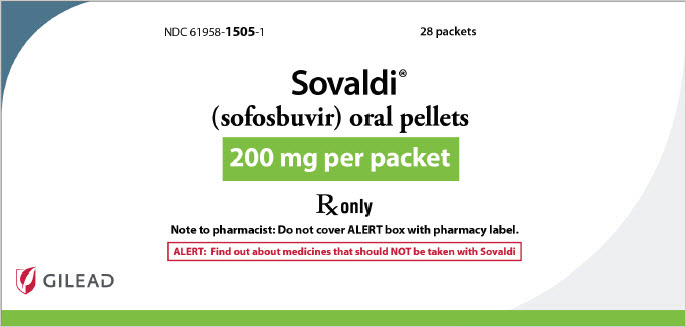 DRUG LABEL: Sovaldi
NDC: 61958-1501 | Form: TABLET, FILM COATED
Manufacturer: Gilead Sciences, Inc.
Category: prescription | Type: HUMAN PRESCRIPTION DRUG LABEL
Date: 20241226

ACTIVE INGREDIENTS: SOFOSBUVIR 400 mg/1 1
INACTIVE INGREDIENTS: MANNITOL; MICROCRYSTALLINE CELLULOSE; CROSCARMELLOSE SODIUM; SILICON DIOXIDE; MAGNESIUM STEARATE; POLYVINYL ALCOHOL, UNSPECIFIED; TITANIUM DIOXIDE; POLYETHYLENE GLYCOL, UNSPECIFIED; TALC; FERRIC OXIDE YELLOW; WATER

HIGHLIGHTS OF PRESCRIBING INFORMATION

These highlights do not include all the information needed to use SOVALDI safely and effectively. See full prescribing information for SOVALDI.
SOVALDI® (sofosbuvir) tablets, for oral use
SOVALDI® (sofosbuvir) oral pellets
Initial U.S. Approval: 2013

WARNING: RISK OF HEPATITIS B VIRUS REACTIVATION IN PATIENTS COINFECTED WITH HCV AND HBV

See full prescribing information for complete boxed warning.

Hepatitis B virus (HBV) reactivation has been reported, in some cases resulting in fulminant hepatitis, hepatic failure, and death. (5.1)

1 INDICATIONS AND USAGE

SOVALDI is a hepatitis C virus (HCV) nucleotide analog NS5B polymerase inhibitor indicated for the treatment of:

- Adult patients with genotype 1, 2, 3 or 4 chronic HCV infection without cirrhosis or with compensated cirrhosis as a component of a combination antiviral treatment regimen. (1)
- Pediatric patients 3 years of age and older with genotype 2 or 3 chronic HCV infection without cirrhosis or with compensated cirrhosis in combination with ribavirin. (1)

2 DOSAGE AND ADMINISTRATION

- Testing Prior to the Initiation of Therapy: Test all patients for HBV infection by measuring HBsAg and anti-HBc. (2.1)
- Recommended dosage in adults: One 400 mg tablet taken once daily with or without food. (2.2)
- Recommended dosage in pediatric patients 3 years of age and older: Recommended dosage of SOVALDI in pediatric patients 3 years of age and older with genotype 2 or 3 HCV using SOVALDI tablets or oral pellets is based on weight. Refer to Table 3 of the full prescribing information for specific dosing guidelines based on body weight. (2.3)
- HCV/HIV-1 coinfection: For adult and pediatric patients with HCV/HIV-1 coinfection, follow the dosage recommendations in the tables below, respectively. (2.2, 2.3)
- Recommended adult treatment regimen and duration: (2.2)

 | Adult Patient Population | Regimen and Duration
Genotype 1 or 4 | Treatment-naïve without cirrhosis or with compensated cirrhosis (Child-Pugh A) | SOVALDI + peginterferon alfa + ribavirin 12 weeks
Genotype 2 | Treatment-naïve and treatment-experienced without cirrhosis or with compensated cirrhosis (Child-Pugh A) | SOVALDI + ribavirin 12 weeks
Genotype 3 | Treatment-naïve and treatment-experienced without cirrhosis or with compensated cirrhosis (Child-Pugh A) | SOVALDI + ribavirin 24 weeks

- SOVALDI in combination with ribavirin for 24 weeks can be considered for adult patients with genotype 1 infection who are interferon ineligible. (2.2)
- Should be used in combination with ribavirin for treatment of HCV in adult patients with hepatocellular carcinoma awaiting liver transplantation for up to 48 weeks or until liver transplantation, whichever occurs first. (2.2)
- Recommended treatment regimen and duration for pediatric patients 3 years of age and older: (2.3, 2.4)

 | Pediatric Patient Population 3 Years of Age and Older | Regimen and Duration
Genotype 2 | Treatment-naïve and treatment-experienced without cirrhosis or with compensated cirrhosis (Child-Pugh A) | SOVALDI + ribavirin 12 weeks
Genotype 3 | Treatment-naïve and treatment-experienced without cirrhosis or with compensated cirrhosis (Child-Pugh A) | SOVALDI + ribavirin 24 weeks

- A dosage recommendation cannot be made for patients with severe renal impairment or end stage renal disease. (2.7, 8.6)
- Instructions for Use should be followed for preparation and administration of SOVALDI oral pellets. (2.4)

3 DOSAGE FORMS AND STRENGTHS

- Tablets: 400 mg and 200 mg of sofosbuvir. (3)
- Oral Pellets: 200 mg and 150 mg of sofosbuvir. (3)

4 CONTRAINDICATIONS

- When used in combination with peginterferon alfa/ribavirin or ribavirin alone, all contraindications to peginterferon alfa and/or ribavirin also apply to SOVALDI combination therapy. (4)

5 WARNINGS AND PRECAUTIONS

- Risk of Hepatitis B Virus Reactivation: Test all patients for evidence of current or prior HBV infection before initiation of HCV treatment. Monitor HCV/HBV coinfected patients for HBV reactivation and hepatitis flare during HCV treatment and post-treatment follow-up. Initiate appropriate patient management for HBV infection as clinically indicated. (5.1)
- Bradycardia with amiodarone coadministration: Serious symptomatic bradycardia may occur in patients taking amiodarone with a sofosbuvir-containing regimen, particularly in patients also receiving beta blockers, or those with underlying cardiac comorbidities and/or advanced liver disease. Coadministration of amiodarone with SOVALDI is not recommended. In patients without alternative, viable treatment options, cardiac monitoring is recommended. (5.2, 6.2, 7.1)

6 ADVERSE REACTIONS

- The most common adverse events (incidence greater than or equal to 20%, all grades) observed with SOVALDI in combination with ribavirin were fatigue and headache. The most common adverse events observed with SOVALDI in combination with peginterferon alfa and ribavirin were fatigue, headache, nausea, insomnia and anemia. (6.1). The most common adverse events observed with SOVALDI in combination with ribavirin oral solution in pediatric patients was decreased appetite. (6.1)

To report SUSPECTED ADVERSE REACTIONS, contact Gilead Sciences, Inc. at 1-800-GILEAD-5 or FDA at 1-800-FDA-1088 or www.fda.gov/medwatch.

7 DRUG INTERACTIONS

- Coadministration of amiodarone with a sofosbuvir-containing regimen may result in serious symptomatic bradycardia. (5.2, 6.2, 7.1)
- Drugs that are intestinal P-gp inducers (e.g., rifampin, St. John's wort) may alter the concentrations of sofosbuvir. (5.3, 7, 12.3)
- Consult the full prescribing information prior to use for potential drug-drug interactions. (5.2, 5.3, 7, 12.3)
- Clearance of HCV infection with direct acting antivirals may lead to changes in hepatic function, which may impact safe and effective use of concomitant medications. Frequent monitoring of relevant laboratory parameters (INR or blood glucose) and dose adjustments of certain concomitant medications may be necessary. (7.1)

8 USE IN SPECIFIC POPULATIONS

- Patients with HCV/HIV-1 coinfection: Safety and efficacy have been studied. (14.4)
- Patients with hepatocellular carcinoma awaiting liver transplantation: Safety and efficacy have been studied. (8.8)

FULL PRESCRIBING INFORMATION

WARNING: RISK OF HEPATITIS B VIRUS REACTIVATION IN PATIENTS COINFECTED WITH HCV AND HBV

Test all patients for evidence of current or prior hepatitis B virus (HBV) infection before initiating treatment with SOVALDI. HBV reactivation has been reported in HCV/HBV coinfected patients who were undergoing or had completed treatment with HCV direct acting antivirals and were not receiving HBV antiviral therapy. Some cases have resulted in fulminant hepatitis, hepatic failure, and death. Monitor HCV/HBV coinfected patients for hepatitis flare or HBV reactivation during HCV treatment and post-treatment follow-up. Initiate appropriate patient management for HBV infection as clinically indicated [see Warnings and Precautions (5.1)].

1 INDICATIONS AND USAGE

Adult Patients:

SOVALDI is indicated for the treatment of adult patients with chronic hepatitis C virus (HCV) infection as a component of a combination antiviral treatment regimen [see Dosage and Administration (2.2), and Clinical Studies (14)]:

- genotype 1 or 4 infection without cirrhosis or with compensated cirrhosis for use in combination with pegylated interferon and ribavirin
- genotype 2 or 3 infection without cirrhosis or with compensated cirrhosis for use in combination with ribavirin.

Pediatric Patients:

SOVALDI is indicated for the treatment of chronic HCV genotype 2 or 3 infection in pediatric patients 3 years of age and older without cirrhosis or with compensated cirrhosis for use in combination with ribavirin [see Dosage and Administration (2.3) and Clinical Studies (14.5)].

2 DOSAGE AND ADMINISTRATION

2.1 Testing Prior to the Initiation of Therapy

Test all patients for evidence of current or prior HBV infection by measuring hepatitis B surface antigen (HBsAg) and hepatitis B core antibody (anti-HBc) before initiating HCV treatment with SOVALDI [see Warnings and Precautions (5.1)].

2.2 Recommended Dosage in Adults

The recommended dosage of SOVALDI is one 400 mg tablet, taken orally, once daily with or without food [see Clinical Pharmacology (12.3)].

Administer SOVALDI in combination with ribavirin or in combination with pegylated interferon and ribavirin for the treatment of HCV. The recommended treatment regimen and duration for SOVALDI combination therapy is provided in Table 1.

For patients with HCV/HIV-1 coinfection, follow the dosage recommendations in Table 1. Refer to Drug Interactions (7) for dosage recommendations for concomitant HIV-1 antiviral drugs.

Table 1 Recommended Treatment Regimen and Duration in Adult Patients with Genotype 1, 2, 3, or 4 HCV
 | Patient Population | Treatment Regimen and Duration
Genotype 1 or 4 | Treatment-naïve without cirrhosis or with compensated cirrhosis (Child-Pugh A) | SOVALDI + peginterferon alfa [See peginterferon alfa prescribing information for dosage recommendation for patients with genotype 1 or 4 HCV.] + ribavirin [Dosage of ribavirin is weight-based (<75 kg = 1000 mg and ≥75 kg = 1200 mg). The daily dosage of ribavirin is administered orally in two divided doses with food. Patients with renal impairment (CrCl ≤50 mL/min) require ribavirin dosage reduction; refer to ribavirin tablet prescribing information.] 12 weeks
Genotype 2 | Treatment-naïve and treatment-experienced [Treatment-experienced patients have failed an interferon-based regimen with or without ribavirin.] without cirrhosis or with compensated cirrhosis (Child-Pugh A) | SOVALDI + ribavirin 12 weeks
Genotype 3 | Treatment-naïve and treatment-experienced without cirrhosis or with compensated cirrhosis (Child-Pugh A) | SOVALDI + ribavirin 24 weeks

Patients with Genotype 1 HCV Who are Ineligible to Receive an Interferon-Based Regimen

SOVALDI in combination with ribavirin for 24 weeks can be considered as a therapeutic option for patients with genotype 1 infection who are ineligible to receive an interferon-based regimen [see Clinical Studies (14.4)]. Treatment decision should be guided by an assessment of the potential benefits and risks for the individual patient.

Patients with Hepatocellular Carcinoma Awaiting Liver Transplantation

Administer SOVALDI in combination with ribavirin for up to 48 weeks or until the time of liver transplantation, whichever occurs first, to prevent post-transplant HCV reinfection [see Use in Specific Populations (8.8)].

2.3 Recommended Dosage in Pediatric Patients 3 Years of Age and Older with Genotype 2 or 3 HCV

The recommended treatment regimen, duration, and recommended dosage for SOVALDI combination therapy is provided in Table 2 and Table 3. Table 4 provides the weight-based dosage of ribavirin when used in combination with SOVALDI for pediatric patients. For patients with HCV/HIV-1 coinfection, follow the dosage recommendations in Table 3 and Table 4. Refer to Drug Interactions (7) for dosage recommendations for concomitant HIV-1 antiviral drugs. In pediatric patients with hepatocellular carcinoma awaiting liver transplantation, administer SOVALDI in combination with ribavirin for up to 48 weeks or until the time of liver transplantation, whichever occurs first, to prevent post-transplant HCV reinfection [see Use in Specific Populations (8.8)].

Table 2 Recommended Treatment Regimen and Duration in Pediatric Patients 3 Years and Older with Genotype 2 or 3 HCV
 | Patient Population | Treatment Regimen and Duration
Genotype 2 | Treatment-naïve and treatment-experienced [Treatment-experienced patients have failed an interferon based regimen with or without ribavirin.] without cirrhosis or with compensated cirrhosis (Child-Pugh A) | SOVALDI + ribavirin [See Table 4 for weight-based ribavirin dosing recommendations.] 12 weeks
Genotype 3 | Treatment-naïve and treatment-experienced without cirrhosis or with compensated cirrhosis (Child-Pugh A) | SOVALDI + ribavirin 24 weeks

The recommended dosage of SOVALDI in pediatric patients 3 years and older with genotype 2 or 3 HCV using SOVALDI tablets or oral pellets (with or without food) is based on weight (Table 3), and is to be taken orally once daily in combination with ribavirin [see Dosage and Administration (2.4), Use in Specific Populations (8.4), Clinical Pharmacology (12.3), and Clinical Studies (14.5)]. SOVALDI pellets can be taken by pediatric patients who cannot swallow the tablet formulation [see Dosage and Administration (2.4)].

Table 3 Dosing for Pediatric Patients 3 Years and Older Using SOVALDI Tablets or Oral Pellets
Body Weight (kg) | Dosing of SOVALDI Tablets or Oral Pellets | SOVALDI Daily Dose
at least 35 | one 400 mg tablet once daily or two 200 mg tablets once daily or two 200 mg packets of pellets once daily | 400 mg per day
17 to less than 35 | one 200 mg tablet once daily or one 200 mg packet of pellets once daily | 200 mg per day
less than 17 | one 150 mg packet of pellets once daily | 150 mg per day

Table 4 Recommended Dosing for Ribavirin in Combination Therapy with SOVALDI for Pediatric Patients 3 Years and Older
Body Weight (kg) | Oral Ribavirin Daily Dosage [The daily dosage of ribavirin is weight-based and is administered orally in two divided doses with food.]
less than 47 | 15 mg per kg per day (divided dose AM and PM)
47–49 | 600 mg per day (1 × 200 mg AM, 2 × 200 mg PM)
50–65 | 800 mg per day (2 × 200 mg AM, 2 × 200 mg PM)
66–80 | 1000 mg per day (2 × 200 mg AM, 3 × 200 mg PM)
greater than 80 | 1200 mg per day (3 × 200 mg AM, 3 × 200 mg PM)

2.4 Preparation and Administration of Oral Pellets

See the SOVALDI oral pellets full Instructions for Use for details on the preparation and administration of SOVALDI pellets.

Do not chew SOVALDI pellets. If SOVALDI pellets are administered with food, sprinkle the pellets on one or more spoonfuls of non-acidic soft food at or below room temperature. Examples of non-acidic foods include pudding, chocolate syrup, mashed potato, and ice cream. Take SOVALDI pellets within 30 minutes of gently mixing with food and swallow the entire contents without chewing to avoid a bitter aftertaste.

2.5 Dosage Modification

Dosage reduction of SOVALDI is not recommended.

If a patient has a serious adverse reaction potentially related to peginterferon alfa and/or ribavirin, the peginterferon alfa and/or ribavirin dosage should be reduced or discontinued, if appropriate, until the adverse reaction abates or decreases in severity. Refer to the peginterferon alfa and ribavirin prescribing information for additional information about how to reduce and/or discontinue the peginterferon alfa and/or ribavirin dosage.

2.6 Discontinuation of Dosing

If the other agents used in combination with SOVALDI are permanently discontinued, SOVALDI should also be discontinued.

2.7 Severe Renal Impairment and End Stage Renal Disease

No dosage recommendation can be given for patients with severe renal impairment (estimated Glomerular Filtration Rate [eGFR] less than 30 mL/min/1.73m^2) or with end stage renal disease (ESRD) due to higher exposures (up to 20-fold) of the predominant sofosbuvir metabolite [see Use in Specific Populations (8.6) and Clinical Pharmacology (12.3)].

3 DOSAGE FORMS AND STRENGTHS

SOVALDI is available as tablets or pellets for oral use. Each dosage form is available in two dose strengths.

- 400 mg Tablets: 400 mg sofosbuvir: yellow, capsule-shaped, film-coated tablet debossed with "GSI" on one side and "7977" on the other side.
- 200 mg Tablets: 200 mg sofosbuvir: yellow, oval-shaped, film-coated tablet debossed with "GSI" on one side and "200" on the other side.
- 200 mg Pellets: 200 mg sofosbuvir: white to off-white pellets in unit-dose packets.
- 150 mg Pellets: 150 mg sofosbuvir: white to off-white pellets in unit-dose packets.

4 CONTRAINDICATIONS

When SOVALDI is used in combination with ribavirin or peginterferon alfa/ribavirin, the contraindications applicable to those agents are applicable to combination therapies. Refer to the prescribing information of peginterferon alfa and ribavirin for a list of their contraindications.

5 WARNINGS AND PRECAUTIONS

5.1 Risk of Hepatitis B Virus Reactivation in Patients Coinfected with HCV and HBV

Hepatitis B virus (HBV) reactivation has been reported in HCV/HBV coinfected patients who were undergoing or had completed treatment with HCV direct acting antivirals, and who were not receiving HBV antiviral therapy. Some cases have resulted in fulminant hepatitis, hepatic failure, and death. Cases have been reported in patients who are HBsAg positive and also in patients with serologic evidence of resolved HBV infection (i.e., HBsAg negative and anti-HBc positive). HBV reactivation has also been reported in patients receiving certain immunosuppressant or chemotherapeutic agents; the risk of HBV reactivation associated with treatment with HCV direct-acting antivirals may be increased in these patients.

HBV reactivation is characterized as an abrupt increase in HBV replication manifesting as a rapid increase in serum HBV DNA level. In patients with resolved HBV infection, reappearance of HBsAg can occur. Reactivation of HBV replication may be accompanied by hepatitis, i.e., increases in aminotransferase levels and, in severe cases, increases in bilirubin levels, liver failure, and death can occur.

Test all patients for evidence of current or prior HBV infection by measuring HBsAg and anti-HBc before initiating HCV treatment with SOVALDI. In patients with serologic evidence of HBV infection, monitor for clinical and laboratory signs of hepatitis flare or HBV reactivation during HCV treatment with SOVALDI and during post-treatment follow-up. Initiate appropriate patient management for HBV infection as clinically indicated.

5.2 Serious Symptomatic Bradycardia When Coadministered with Amiodarone

Postmarketing cases of symptomatic bradycardia and cases requiring pacemaker intervention have been reported when amiodarone is coadministered with a sofosbuvir-containing regimen. A fatal cardiac arrest was reported in a patient taking amiodarone who was coadministered a sofosbuvir-containing regimen (HARVONI [ledipasvir/sofosbuvir]). Bradycardia has generally occurred within hours to days, but cases have been observed up to 2 weeks after initiating HCV treatment. Patients also taking beta blockers, or those with underlying cardiac comorbidities and/or advanced liver disease may be at increased risk for symptomatic bradycardia with coadministration of amiodarone. Bradycardia generally resolved after discontinuation of HCV treatment. The mechanism for this effect is unknown.

Coadministration of amiodarone with SOVALDI is not recommended. For patients taking amiodarone who have no other alternative, viable treatment options and who will be coadministered SOVALDI:

- Counsel patients about the risk of serious symptomatic bradycardia
- Cardiac monitoring in an in-patient setting for the first 48 hours of coadministration is recommended, after which outpatient or self-monitoring of the heart rate should occur on a daily basis through at least the first 2 weeks of treatment.

Patients who are taking SOVALDI who need to start amiodarone therapy due to no other alternative, viable treatment options should undergo similar cardiac monitoring as outlined above.

Due to amiodarone's long half-life, patients discontinuing amiodarone just prior to starting SOVALDI should also undergo similar cardiac monitoring as outlined above.

Patients who develop signs or symptoms of bradycardia should seek medical evaluation immediately. Symptoms may include near-fainting or fainting, dizziness or lightheadedness, malaise, weakness, excessive tiredness, shortness of breath, chest pains, confusion or memory problems [see Adverse Reactions (6.2), Drug Interactions (7.1)].

5.3 Risk of Reduced Therapeutic Effect Due to Use with P-gp Inducers

Drugs that are P-gp inducers in the intestine (e.g., rifampin, St. John's wort) may significantly decrease sofosbuvir plasma concentrations and may lead to a reduced therapeutic effect of SOVALDI. The use of rifampin and St. John's wort with SOVALDI is not recommended [see Drug Interactions (7.1)].

5.4 Risks Associated with Combination Treatment

Because SOVALDI is used in combination with other antiviral drugs for treatment of HCV infection, consult the prescribing information for these drugs used in combination with SOVALDI. Warnings and Precautions related to these drugs also apply to their use in SOVALDI combination treatment.

6 ADVERSE REACTIONS

The following serious adverse reactions are described below and elsewhere in the labeling:

- Serious Symptomatic Bradycardia When Coadministered with Amiodarone [see Warnings and Precautions (5.2)].

6.1 Clinical Trials Experience

Because clinical trials are conducted under widely varying conditions, adverse reaction rates observed in the clinical trials of a drug cannot be directly compared to rates in the clinical trials of another drug and may not reflect the rates observed in practice.

When SOVALDI is administered with ribavirin or peginterferon alfa/ribavirin, refer to the respective prescribing information for a description of adverse reactions associated with their use.

Adverse Reactions in Adult Subjects

The safety assessment of SOVALDI was based on pooled Phase 3 clinical trial data (both controlled and uncontrolled) including:

- 650 subjects who received SOVALDI + ribavirin (RBV) combination therapy for 12 weeks,
- 98 subjects who received SOVALDI + ribavirin combination therapy for 16 weeks,
- 250 subjects who received SOVALDI + ribavirin combination therapy for 24 weeks,
- 327 subjects who received SOVALDI + peginterferon (Peg-IFN) alfa + ribavirin combination therapy for 12 weeks,
- 243 subjects who received peginterferon alfa + ribavirin for 24 weeks, and
- 71 subjects who received placebo (PBO) for 12 weeks [see Clinical Studies (14)].

The proportion of subjects who permanently discontinued treatment due to adverse events was 4% for subjects receiving placebo, 1% for subjects receiving SOVALDI + ribavirin for 12 weeks, less than 1% for subjects receiving SOVALDI + ribavirin for 24 weeks, 11% for subjects receiving peginterferon alfa + ribavirin for 24 weeks and 2% for subjects receiving SOVALDI + peginterferon alfa + ribavirin for 12 weeks.

Adverse events observed in at least 15% of subjects in the Phase 3 clinical trials outlined above are provided in Table 5. A side-by-side tabulation is displayed to simplify presentation; direct comparison across trials should not be made due to differing trial designs.

The most common adverse events (at least 20%) for SOVALDI + ribavirin combination therapy were fatigue and headache. The most common adverse events (at least 20%) for SOVALDI + peginterferon alfa + ribavirin combination therapy were fatigue, headache, nausea, insomnia and anemia.

Table 5 Adverse Events (All Grades and without Regard to Causality) Reported in ≥15% of Subjects with HCV in Any Treatment Arm
 | Interferon-free Regimens |  |  | Interferon-containing Regimens
 | PBO 12 weeks | SOVALDI + RBV [Subjects received weight-based ribavirin (1000 mg per day if weighing <75 kg or 1200 mg per day if weighing ≥75 kg).] 12 weeks | SOVALDI + RBV 24 weeks | Peg-IFN alfa + RBV [Subjects received 800 mg ribavirin per day regardless of weight.] 24 weeks | SOVALDI + Peg-IFN alfa + RBV 12 weeks
 | N=71 | N=650 | N=250 | N=243 | N=327
Fatigue | 24% | 38% | 30% | 55% | 59%
Headache | 20% | 24% | 30% | 44% | 36%
Nausea | 18% | 22% | 13% | 29% | 34%
Insomnia | 4% | 15% | 16% | 29% | 25%
Pruritus | 8% | 11% | 27% | 17% | 17%
Anemia | 0% | 10% | 6% | 12% | 21%
Asthenia | 3% | 6% | 21% | 3% | 5%
Rash | 8% | 8% | 9% | 18% | 18%
Decreased Appetite | 10% | 6% | 6% | 18% | 18%
Chills | 1% | 2% | 2% | 18% | 17%
Influenza Like Illness | 3% | 3% | 6% | 18% | 16%
Pyrexia | 0% | 4% | 4% | 14% | 18%
Diarrhea | 6% | 9% | 12% | 17% | 12%
Neutropenia | 0% | <1% | <1% | 12% | 17%
Myalgia | 0% | 6% | 9% | 16% | 14%
Irritability | 1% | 10% | 10% | 16% | 13%

With the exception of anemia and neutropenia, the majority of events presented in Table 5 occurred at severity of grade 1 in SOVALDI-containing regimens.

Less Common Adverse Reactions Reported in Clinical Trials (less than 1%): The following adverse reactions occurred in less than 1% of subjects receiving SOVALDI in a combination regimen in any one trial. These events have been included because of their seriousness or assessment of potential causal relationship.

Hematologic Effects: pancytopenia (particularly in subjects receiving concomitant pegylated interferon).

Psychiatric Disorders: severe depression (particularly in subjects with pre-existing history of psychiatric illness), including suicidal ideation and suicide.

Laboratory Abnormalities:

Changes in selected hematological parameters are described in Table 6. A side-by-side tabulation is displayed to simplify presentation; direct comparison across trials should not be made due to differing trial designs.

Table 6 Percentage of Subjects Reporting Selected Hematological Parameters
Hematological Parameters | Interferon-free Regimens |  |  | Interferon-containing Regimens
Hematological Parameters | PBO 12 weeks | SOVALDI + RBV [Subjects received weight-based ribavirin (1000 mg per day if weighing <75 kg or 1200 mg per day if weighing ≥75 kg).] 12 weeks | SOVALDI + RBV 24 weeks | Peg-IFN + RBV [Subjects received 800 mg ribavirin per day regardless of weight.] 24 weeks | SOVALDI + Peg-IFN + RBV 12 weeks
 | N=71 | N=647 | N=250 | N=242 | N=327
Hemoglobin (g/dL)
<10 | 0 | 8% | 6% | 14% | 23%
<8.5 | 0 | 1% | <1% | 2% | 2%
Neutrophils (×10^9/L)
≥0.5 – <0.75 | 1% | <1% | 0 | 12% | 15%
<0.5 | 0 | <1% | 0 | 2% | 5%
Platelets (×10^9/L)
≥25 – <50 | 3% | <1% | 1% | 7% | <1%
<25 | 0 | 0 | 0 | 0 | 0

Bilirubin Elevations

Total bilirubin elevation of more than 2.5×ULN was observed in none of the subjects in the SOVALDI + peginterferon alfa + ribavirin 12 weeks group and in 1%, 3% and 3% of subjects in the peginterferon alfa + ribavirin 24 weeks, SOVALDI + ribavirin 12 weeks and SOVALDI + ribavirin 24 weeks groups, respectively. Bilirubin levels peaked during the first 1 to 2 weeks of treatment and subsequently decreased and returned to baseline levels by post-treatment Week 4. These bilirubin elevations were not associated with transaminase elevations.

Creatine Kinase Elevations

Creatine kinase was assessed in the FISSION and NEUTRINO trials. Isolated, asymptomatic creatine kinase elevation of greater than or equal to 10×ULN was observed in less than 1%, 1% and 2% of subjects in the peginterferon alfa + ribavirin 24 weeks, SOVALDI + peginterferon alfa + ribavirin 12 weeks and SOVALDI + ribavirin 12 weeks groups, respectively.

Lipase Elevations

Isolated, asymptomatic lipase elevation of greater than 3×ULN was observed in less than 1%, 2%, 2%, and 2% of subjects in the SOVALDI + peginterferon alfa + ribavirin 12 weeks, SOVALDI + ribavirin 12 weeks, SOVALDI + ribavirin 24 weeks and peginterferon alfa + ribavirin 24 weeks groups, respectively.

Patients with HCV/HIV-1 Coinfection

SOVALDI used in combination with ribavirin was assessed in 223 HCV/HIV-1 coinfected subjects [see Clinical Studies (14.4)]. The safety profile in HCV/HIV-1 coinfected subjects was similar to that observed in HCV mono-infected subjects. Elevated total bilirubin (grade 3 or 4) was observed in 30/32 (94%) subjects receiving atazanavir as part of the antiretroviral regimen. None of the subjects had concomitant transaminase increases. Among subjects not taking atazanavir, grade 3 or 4 elevated total bilirubin was observed in 2 (1.5%) subjects, similar to the rate observed with HCV mono-infected subjects receiving SOVALDI + ribavirin in Phase 3 trials.

Adverse Reactions in Pediatric Subjects 3 Years of Age and Older

The safety assessment of SOVALDI in pediatric subjects 3 years of age and older is based on data from 106 subjects who were treated with SOVALDI plus ribavirin for 12 weeks (genotype 2 subjects) or 24 weeks (genotype 3 subjects) in a Phase 2, open-label clinical trial. The adverse reactions observed were consistent with those observed in clinical studies of SOVALDI plus ribavirin in adults. Among pediatric subjects 3 years to < 12 years of age taking SOVALDI in combination with ribavirin oral solution, decreased appetite was observed in 13% (7/54) of subjects [see Clinical Studies 14.5)].

In a 5-year follow-up study, 88 of the 106 subjects from the Phase 2 open-label clinical trial (Study 1112) were followed for a median (Q1, Q3) duration of 239 (179, 244) weeks. No notable effects on growth as assessed by changes from baseline through end of study were observed for height, weight, BMI percentiles, and Z-scores for any age group. No notable effects were observed on the development of secondary sexual characteristics of subjects as assessed by changes from baseline through end of study in Tanner pubertal stages [see Use in Specific Populations (8.4)].

6.2 Postmarketing Experience

The following adverse reactions have been identified during post approval use of SOVALDI. Because postmarketing reactions are reported voluntarily from a population of uncertain size, it is not always possible to reliably estimate their frequency or establish a causal relationship to drug exposure.

Cardiac Disorders

Serious symptomatic bradycardia has been reported in patients taking amiodarone who initiate treatment with a sofosbuvir-containing regimen [see Warnings and Precautions (5.2), Drug Interactions (7.1)].

Skin and Subcutaneous Tissue Disorders

Skin rashes, sometimes with blisters or angioedema-like swelling
Angioedema

7 DRUG INTERACTIONS

7.1 Potentially Significant Drug Interactions

Sofosbuvir is a substrate of drug transporter P-gp and breast cancer resistance protein (BCRP) while the predominant circulating metabolite GS-331007 is not. Drugs that are P-gp inducers in the intestine (e.g., rifampin or St. John's wort) may decrease sofosbuvir plasma concentration, leading to reduced therapeutic effect of SOVALDI, and thus concomitant use with SOVALDI is not recommended [see Warnings and Precautions (5.3)].

Clearance of HCV infection with direct acting antivirals may lead to changes in hepatic function, which may impact the safe and effective use of concomitant medications. For example, altered blood glucose control resulting in serious symptomatic hypoglycemia has been reported in diabetic patients in postmarketing case reports and published epidemiological studies. Management of hypoglycemia in these cases required either discontinuation or dose modification of concomitant medications used for diabetes treatment.

Frequent monitoring of relevant laboratory parameters (e.g. International Normalized Ratio [INR] in patients taking warfarin, blood glucose levels in diabetic patients) or drug concentrations of concomitant medications such as cytochrome P450 substrates with a narrow therapeutic index (e.g. certain immunosuppressants) is recommended to ensure safe and effective use. Dose adjustments of concomitant medications may be necessary.

Information on potential drug interactions with SOVALDI is summarized in Table 7. The table is not all-inclusive [see Warnings and Precautions (5.2, 5.3) and Clinical Pharmacology (12.3)].

Table 7 Potentially Significant Drug Interactions: Alteration in Dosage or Regimen May Be Recommended Based on Drug Interaction Studies or Predicted Interaction [This table is not all-inclusive.]
Concomitant Drug Class: Drug Name | Effect on Concentration [↓ = decrease.] | Clinical Comment
Antiarrhythmics: amiodarone | Effect on amiodarone and sofosbuvir concentrations unknown | Coadministration of amiodarone with a sofosbuvir-containing regimen may result in serious symptomatic bradycardia. The mechanism of this effect is unknown. Coadministration of amiodarone with SOVALDI is not recommended; if coadministration is required, cardiac monitoring is recommended [see Warnings and Precautions (5.2), Adverse Reactions (6.2)].
Anticonvulsants: Carbamazepine phenytoin phenobarbital oxcarbazepine | ↓ sofosbuvir ↓ GS-331007 | Coadministration of SOVALDI with carbamazepine, phenytoin, phenobarbital or oxcarbazepine is expected to decrease the concentration of sofosbuvir, leading to reduced therapeutic effect of SOVALDI. Coadministration is not recommended.
Antimycobacterials: Rifabutin rifampin rifapentine | ↓ sofosbuvir ↓ GS-331007 | Coadministration of SOVALDI with rifabutin or rifapentine is expected to decrease the concentration of sofosbuvir, leading to reduced therapeutic effect of SOVALDI. Coadministration is not recommended. Coadministration of SOVALDI with rifampin, an intestinal P-gp inducer, is not recommended [see Warnings and Precautions (5.3)].
Herbal Supplements: St. John's wort (Hypericum perforatum) | ↓ sofosbuvir ↓ GS-331007 | Coadministration of SOVALDI with St. John's wort, an intestinal P-gp inducer, is not recommended [see Warnings and Precautions (5.3)].
HIV Protease Inhibitors: tipranavir/ritonavir | ↓ sofosbuvir ↓ GS-331007 | Coadministration of SOVALDI with tipranavir/ritonavir is expected to decrease the concentration of sofosbuvir, leading to reduced therapeutic effect of SOVALDI. Coadministration is not recommended.

7.2 Drugs without Clinically Significant Interactions with SOVALDI

Based on drug interaction studies conducted with SOVALDI, no clinically significant drug interactions have been either observed or are expected when SOVALDI is combined with the following drugs [see Clinical Pharmacology (12.3)]: cyclosporine, darunavir/ritonavir, efavirenz, emtricitabine, methadone, oral contraceptives, raltegravir, rilpivirine, tacrolimus, or tenofovir disoproxil fumarate.

8 USE IN SPECIFIC POPULATIONS

8.1 Pregnancy

Risk Summary

If SOVALDI is administered with ribavirin or peginterferon alfa and ribavirin, the combination regimen is contraindicated in pregnant women and in men whose female partners are pregnant. Refer to the ribavirin and/or peginterferon alfa prescribing information for more information on ribavirin- and peginterferon alfa-associated risks of use during pregnancy.

No adequate human data are available to establish whether or not SOVALDI poses a risk to pregnancy outcomes. In animal reproduction studies, no evidence of adverse developmental outcomes was observed with sofosbuvir at exposures greater than those in humans at the recommended human dose (RHD) [see Data]. During organogenesis in the rat and rabbit, systemic exposures (AUC) to the predominant circulating metabolite of sofosbuvir (GS-331007) were ≥5 (rats) and 12 (rabbits) times the exposure in humans at the RHD. In the rat pre/postnatal development study, maternal systemic exposure (AUC) to GS-331007 was ≥6 times the exposure in humans at the RHD.

The background risk of major birth defects and miscarriage for the indicated population is unknown. In the U.S. general population, the estimated background risk of major birth defects and miscarriage in clinically recognized pregnancies is 2–4% and 15–20%, respectively.

Data

Animal Data

Sofosbuvir was administered orally to pregnant rats (up to 500 mg/kg/day) and rabbits (up to 300 mg/kg/day) on gestation days 6 to 18 and 6 to 19, respectively, and also to rats (oral doses up to 500 mg/kg/day) on gestation day 6 to lactation/post-partum day 20. No significant effects on embryo-fetal (rats and rabbits) or pre/postnatal (rats) development were observed at the highest doses tested. Systemic exposures (AUC) to the predominant circulating metabolite of sofosbuvir (GS-331007) were ≥5 (rats) and 12 (rabbits) times the exposure in humans at the RHD, with exposures increasing during gestation from approximately 5 to 10 (rats) and 12 to 28 (rabbits) times the exposure in humans at the RHD.

8.2 Lactation

Risk Summary

It is not known whether sofosbuvir or its metabolites are present in human breast milk, affect human milk production or have effects on the breastfed infant. The predominant circulating metabolite of sofosbuvir (GS-331007) was the primary component observed in the milk of lactating rats, without effect on nursing pups [see Data].

The developmental and health benefits of breastfeeding should be considered along with the mother's clinical need for SOVALDI and any potential adverse effects on the breastfed child from SOVALDI or from the underlying maternal condition.

If SOVALDI is administered with ribavirin, the nursing mother's information for ribavirin also applies to this combination regimen. Refer to the ribavirin prescribing information for more information on use during lactation.

Data

Animal Data

No effects of sofosbuvir on growth and postnatal development were observed in nursing pups at the highest dose tested in rats. Maternal systemic exposure (AUC) to the predominant circulating metabolite of sofosbuvir (GS-331007) was approximately 12 times the exposure in humans at the RHD, with exposure of approximately 2% that of maternal exposure observed in nursing pups on lactation day 10. In a lactation study, sofosbuvir metabolites (primarily GS-331007) were excreted into the milk of lactating rats following administration of a single oral dose of sofosbuvir (20 mg/kg) on lactation day 2, with milk concentrations of approximately 10% that of maternal plasma concentrations observed 1 hour post-dose.

8.3 Females and Males of Reproductive Potential

If SOVALDI is administered with ribavirin or peginterferon and ribavirin, the information for ribavirin and peginterferon with regard to pregnancy testing, contraception, and infertility also applies to these combination regimens. Refer to ribavirin and/or peginterferon prescribing information for additional information.

8.4 Pediatric Use

The safety, pharmacokinetics, and efficacy of SOVALDI in pediatric patients 3 years of age and older with genotype 2 and 3 infection have been established. SOVALDI was evaluated in an open-label clinical trial (Study 1112), which included 106 subjects (31 genotype 2; 75 genotype 3) 3 years of age and older. The safety, pharmacokinetics, and efficacy were comparable to that observed in adults [see Dosage and Administration (2.3), Adverse Reactions (6.1), Clinical Pharmacology (12.3), and Clinical Studies (14.5)].

The safety and efficacy of SOVALDI in pediatric patients 3 years of age and older with compensated cirrhosis is supported by comparable sofosbuvir and GS-331007 exposures between: 1) adults and pediatric patients without cirrhosis and 2) adults without cirrhosis and adults with compensated cirrhosis. Thus, similar efficacy would be expected for pediatric patients with compensated cirrhosis as adults with compensated cirrhosis.

The safety and efficacy of SOVALDI have not been established in pediatric patients less than 3 years of age with HCV genotype 2 or 3. The safety and efficacy of SOVALDI have not been established in pediatric patients with HCV genotype 1 or 4.

In a 5-year follow-up study, the long-term effects of SOVALDI on pediatric growth were assessed in 88 pediatric subjects 3 years of age and older treated with SOVALDI in Study 1112. No notable effects on growth from baseline through end of study were observed [see Adverse Reactions (6.1)]. All subjects who had achieved SVR12 maintained SVR through end of study.

8.5 Geriatric Use

SOVALDI was administered to 90 subjects aged 65 and over. The response rates observed for subjects over 65 years of age were similar to that of younger subjects across treatment groups. No dosage adjustment of SOVALDI is warranted in geriatric patients [see Clinical Pharmacology (12.3)].

8.6 Renal Impairment

No dosage adjustment of SOVALDI is required for patients with mild or moderate renal impairment. The safety and efficacy of SOVALDI have not been established in patients with severe renal impairment (eGFR less than 30 mL/min/1.73m^2) or ESRD requiring hemodialysis. No dosage recommendation can be given for patients with severe renal impairment or ESRD [see Dosage and Administration (2.7) and Clinical Pharmacology (12.3)]. Refer also to ribavirin and peginterferon alfa prescribing information for patients with CrCl less than 50 mL/min.

8.7 Hepatic Impairment

No dosage adjustment of SOVALDI is required for patients with mild, moderate or severe hepatic impairment (Child-Pugh Class A, B or C) [see Clinical Pharmacology (12.3)]. Safety and efficacy of SOVALDI have not been established in patients with decompensated cirrhosis. See peginterferon alfa prescribing information for contraindication in hepatic decompensation.

8.8 Patients with Hepatocellular Carcinoma Awaiting Liver Transplantation

SOVALDI was studied in HCV-infected adult subjects with hepatocellular carcinoma prior to undergoing liver transplantation in an open-label clinical trial evaluating the safety and efficacy of SOVALDI and ribavirin administered pre-transplant to prevent post-transplant HCV reinfection. The primary endpoint of the trial was post-transplant virologic response (pTVR) defined as HCV RNA less than lower limit of quantification (LLOQ) at 12 weeks post-transplant. HCV-infected subjects, regardless of genotype, with hepatocellular carcinoma (HCC) meeting the MILAN criteria (defined as the presence of a tumor 5 cm or less in diameter in patients with single hepatocellular carcinomas and no more than three tumor nodules, each 3 cm or less in diameter in patients with multiple tumors and no extrahepatic manifestations of the cancer or evidence of vascular invasion of tumor) received 400 mg SOVALDI and weight-based 1000–1200 mg ribavirin daily for 24–48 weeks or until the time of liver transplantation, whichever occurred first. An interim analysis was conducted on 61 subjects who received SOVALDI and ribavirin; 45 subjects had HCV genotype 1; 44 subjects had a baseline CPT score less than 7 and all subjects had a baseline unadjusted MELD score up to 14. Of these 61 subjects, 41 subjects underwent liver transplantation following up to 48 weeks of treatment with SOVALDI and ribavirin; 37 had HCV RNA less than LLOQ at the time of transplantation. Of the 37 subjects, the post-transplant virologic response (pTVR) rate is 64% (23/36) in the 36 evaluable subjects who have reached the 12 week post-transplant time point. The safety profile of SOVALDI and ribavirin in HCV-infected subjects prior to liver transplantation was comparable to that observed in subjects treated with SOVALDI and ribavirin in Phase 3 clinical trials.

8.9 Post-Liver Transplant Patients

The safety and efficacy of SOVALDI have not been established in post-liver transplant patients.

8.10 Patients with Genotype 5 or 6 HCV Infection

Available data on subjects with genotype 5 or 6 HCV infection are insufficient for dosing recommendations.

10 OVERDOSAGE

The highest documented dosage of sofosbuvir was a single dose of sofosbuvir 1200 mg (three times the recommended dosage) administered to 59 healthy subjects. In that trial, there were no untoward effects observed at this dosage level, and adverse events were similar in frequency and severity to those reported in the placebo and sofosbuvir 400 mg treatment groups. The effects of higher dosages are not known.

No specific antidote is available for overdose with SOVALDI. If overdose occurs, the patient must be monitored for evidence of toxicity. Treatment of overdose with SOVALDI consists of general supportive measures including monitoring of vital signs as well as observation of the clinical status of the patient. A 4-hour hemodialysis session removed 18% of the administered dose.

11 DESCRIPTION

SOVALDI (sofosbuvir) is a nucleotide analog inhibitor of HCV NS5B polymerase.

The IUPAC name for sofosbuvir is (S)-isopropyl 2-((S)-(((2R,3R,4R,5R)-5-(2,4-dioxo-3,4-dihydropyrimidin-1(2H)-yl)-4-fluoro-3-hydroxy-4-methyltetrahydrofuran-2-yl)methoxy)-(phenoxy)phosphorylamino)propanoate. It has a molecular formula of C22H29FN3O9P and a molecular weight of 529.45. It has the following structural formula:

Sofosbuvir is a white to off-white crystalline solid with a solubility of ≥ 2 mg/mL across the pH range of 2–7.7 at 37 °C and is slightly soluble in water.

SOVALDI tablets, 200 mg or 400 mg, are for oral administration. Each tablet contains 200 mg or 400 mg of sofosbuvir. The tablets include the following inactive ingredients: colloidal silicon dioxide, croscarmellose sodium, magnesium stearate, mannitol, and microcrystalline cellulose. The tablets are film-coated with a coating material containing the following inactive ingredients: polyethylene glycol, polyvinyl alcohol, talc, titanium dioxide, and yellow iron oxide.

SOVALDI pellets, 150 mg or 200 mg, are for oral administration, supplied as white to off-white pellets in unit-dose packets. Each unit-dose packet contains 150 mg or 200 mg of sofosbuvir. The pellets include the following inactive ingredients: amino methacrylate copolymer, colloidal silicon dioxide, croscarmellose sodium, hydroxypropyl cellulose, hypromellose, lactose monohydrate, microcrystalline cellulose, polyethylene glycol, silicon dioxide, sodium lauryl sulfate, sodium stearyl fumarate, stearic acid, and talc.

12 CLINICAL PHARMACOLOGY

12.1 Mechanism of Action

Sofosbuvir is a direct-acting antiviral agent against the hepatitis C virus [see Microbiology (12.4)].

12.2 Pharmacodynamics

Cardiac Electrophysiology

The effect of sofosbuvir 400 and 1200 mg (three times the recommended dosage) on QTc interval was evaluated in a randomized, single-dose, placebo- and active-controlled (moxifloxacin 400 mg) four period crossover thorough QT trial in 59 healthy subjects. At a dosage three times the maximum recommended dosage, SOVALDI does not prolong QTc to any clinically relevant extent.

12.3 Pharmacokinetics

Absorption

The pharmacokinetic properties of sofosbuvir and the predominant circulating metabolite GS-331007 have been evaluated in healthy adult subjects and in subjects with chronic hepatitis C. Following oral administration of SOVALDI, sofosbuvir was absorbed with a peak plasma concentration observed at ~0.5–2 hour post-dose, regardless of dose level. Peak plasma concentration of GS-331007 was observed between 2 to 4 hours post-dose. Based on population pharmacokinetic analysis in subjects with genotype 1 to 6 HCV infection who were coadministered ribavirin (with or without pegylated interferon), geometric mean steady state AUC0–24 was 969 ng∙hr/mL for sofosbuvir (N=838), and 6790 ng∙hr/mL for GS-331007 (N=1695). Relative to healthy subjects administered sofosbuvir alone (N=272), the sofosbuvir AUC0–24 was 60% higher; and GS-331007 AUC0–24 was 39% lower, respectively, in HCV-infected subjects. Sofosbuvir and GS-331007 AUCs are near dose proportional over the dose range of 200 mg to 1200 mg.

Effect of Food

Relative to fasting conditions, the administration of a single dose of SOVALDI with a standardized high fat meal did not substantially affect the sofosbuvir Cmax or AUC0–inf. The exposure of GS-331007 was not altered in the presence of a high-fat meal. Therefore, SOVALDI can be administered without regard to food.

Distribution

Sofosbuvir is approximately 61–65% bound to human plasma proteins and the binding is independent of drug concentration over the range of 1 microgram/mL to 20 microgram/mL. Protein binding of GS-331007 was minimal in human plasma. After a single 400 mg dose of [^14C]-sofosbuvir in healthy subjects, the blood to plasma ratio of ^14C-radioactivity was approximately 0.7.

Metabolism

Sofosbuvir is extensively metabolized in the liver to form the pharmacologically active nucleoside analog triphosphate GS-461203. The metabolic activation pathway involves sequential hydrolysis of the carboxyl ester moiety catalyzed by human cathepsin A (CatA) or carboxylesterase 1 (CES1) and phosphoramidate cleavage by histidine triad nucleotide-binding protein 1 (HINT1) followed by phosphorylation by the pyrimidine nucleotide biosynthesis pathway. Dephosphorylation results in the formation of nucleoside metabolite GS-331007 that cannot be efficiently rephosphorylated and lacks anti-HCV activity in vitro.

After a single 400 mg oral dose of [^14C]-sofosbuvir, sofosbuvir and GS-331007 accounted for approximately 4% and greater than 90% of drug related material (sum of molecular weight-adjusted AUC of sofosbuvir and its metabolites) systemic exposure, respectively.

Elimination

Following a single 400 mg oral dose of [^14C]-sofosbuvir, mean total recovery of the dose was greater than 92%, consisting of approximately 80%, 14%, and 2.5% recovered in urine, feces, and expired air, respectively. The majority of the sofosbuvir dose recovered in urine was GS-331007 (78%) while 3.5% was recovered as sofosbuvir. These data indicate that renal clearance is the major elimination pathway for GS-331007. The median terminal half-lives of sofosbuvir and GS-331007 were 0.4 and 27 hours, respectively.

Specific Populations

Race

Population pharmacokinetics analysis in HCV-infected subjects indicated that race had no clinically relevant effect on the exposure of sofosbuvir and GS-331007.

Gender

No clinically relevant pharmacokinetic differences have been observed between men and women for sofosbuvir and GS-331007.

Pediatric Patients

The pharmacokinetics of sofosbuvir and GS-331007 were determined in HCV genotype 2 or 3 infected pediatric subjects 3 years of age and older receiving a daily dose of SOVALDI as described in Table 8. Exposures in pediatric subjects were similar to those observed in adults.

Table 8 Pharmacokinetic Properties of SOVALDI in HCV-infected Pediatric Subjects 3 Years of Age and Older [Population PK derived parameters]
Weight Group | Dose | PK Parameter | Geometric Mean (%CV)
Weight Group | Dose | PK Parameter | Sofosbuvir | GS-331007
≥35 kg [Sofosbuvir N=28; GS-331007 N=50] | 400 mg | AUCtau (ng∙hr/mL) | 1060 (50.6) | 7570 (32.8)
≥35 kg [Sofosbuvir N=28; GS-331007 N=50] | 400 mg | Cmax (ng/mL) | 472 (53.0) | 572 (40.7)
17 to <35 kg [Sofosbuvir N=29; GS-331007 N=30] | 200 mg | AUCtau (ng∙hr/mL) | 891 (36.1) | 10400 (31.6)
17 to <35 kg [Sofosbuvir N=29; GS-331007 N=30] | 200 mg | Cmax (ng/mL) | 438 (26.4) | 866 (27.1)
<17 kg [Sofosbuvir N=7; GS-331007 N=7] | 150 mg | AUCtau (ng∙hr/mL) | 851 (41.7) | 9060 (37.6)
<17 kg [Sofosbuvir N=7; GS-331007 N=7] | 150 mg | Cmax (ng/mL) | 418 (26.8) | 767 (28.3)

The pharmacokinetics of sofosbuvir and GS-331007 have not been established in pediatric subjects less than 3 years of age [see Use in Specific Populations (8.4) and Clinical Studies (14.5)].

Geriatric Patients

Population pharmacokinetic analysis in HCV-infected subjects showed that within the age range (19 to 75 years) analyzed, age did not have a clinically relevant effect on the exposure to sofosbuvir and GS-331007 [see Use in Specific Populations (8.5)].

Patients with Renal Impairment

The pharmacokinetics of sofosbuvir were studied in HCV negative subjects with mild (eGFR between 50 to less than 80 mL/min/1.73m^2), moderate (eGFR between 30 to less than 50 mL/min/1.73m^2), severe renal impairment (eGFR less than 30 mL/min/1.73m^2) and subjects with end stage renal disease (ESRD) requiring hemodialysis following a single 400 mg dose of sofosbuvir. Relative to subjects with normal renal function (eGFR greater than 80 mL/min/1.73m^2), the sofosbuvir AUC0–inf was 61%, 107% and 171% higher in mild, moderate and severe renal impairment, while the GS-331007 AUC0–inf was 55%, 88% and 451% higher, respectively. In subjects with ESRD, relative to subjects with normal renal function, sofosbuvir and GS-331007 AUC0–inf was 28% and 1280% higher when sofosbuvir was dosed 1 hour before hemodialysis compared with 60% and 2070% higher when sofosbuvir was dosed 1 hour after hemodialysis, respectively. A 4 hour hemodialysis session removed approximately 18% of administered dose. No dosage adjustment is required for patients with mild or moderate renal impairment. The safety and efficacy of SOVALDI have not been established in patients with severe renal impairment or ESRD. No dosage recommendation can be given for patients with severe renal impairment or ESRD [see Dosage and Administration (2.6) and Use in Specific Populations (8.6)].

Patients with Hepatic Impairment

The pharmacokinetics of sofosbuvir were studied following 7-day dosing of 400 mg sofosbuvir in HCV-infected subjects with moderate and severe hepatic impairment (Child-Pugh Class B and C). Relative to subjects with normal hepatic function, the sofosbuvir AUC0–24 were 126% and 143% higher in moderate and severe hepatic impairment, while the GS-331007 AUC0–24 were 18% and 9% higher, respectively. Population pharmacokinetics analysis in HCV-infected subjects indicated that cirrhosis had no clinically relevant effect on the exposure of sofosbuvir and GS-331007. No dosage adjustment of SOVALDI is recommended for patients with mild, moderate or severe hepatic impairment [see Use in Specific Populations (8.7)].

Assessment of Drug Interactions

Sofosbuvir is a substrate of drug transporter P-gp and breast cancer resistance protein (BCRP) while GS-331007 is not. Drugs that are P-gp inducers in the intestine (e.g., rifampin or St. John's wort) may decrease sofosbuvir plasma concentration, leading to reduced therapeutic effect of SOVALDI, and thus concomitant use with SOVALDI is not recommended [see Warnings and Precautions (5.3) and Drug Interactions (7.1)].

Coadministration of SOVALDI with drugs that inhibit P-gp and/or BCRP may increase sofosbuvir plasma concentration without increasing GS-331007 plasma concentration; accordingly, SOVALDI may be coadministered with P-gp and/or BCRP inhibitors. Sofosbuvir and GS-331007 are not inhibitors of P-gp and BCRP and thus are not expected to increase exposures of drugs that are substrates of these transporters.

The intracellular metabolic activation pathway of sofosbuvir is mediated by generally low affinity and high capacity hydrolase and nucleotide phosphorylation pathways that are unlikely to be affected by concomitant drugs.

The effects of coadministered drugs on the exposure of sofosbuvir and GS-331007 are shown in Table 9. The effects of sofosbuvir on the exposure of coadministered drugs are shown in Table 10 [see Drug Interactions (7.1, 7.2)].

Table 9 Drug Interactions: Changes in Pharmacokinetic Parameters for Sofosbuvir and the Predominant Circulating Metabolite GS-331007 in the Presence of the Coadministered Drug [All interaction studies conducted in healthy volunteers]
Coadministered Drug | Dose of Coadministered Drug (mg) | Sofosbuvir Dose (mg) | N | Mean Ratio (90% CI) of Sofosbuvir and GS-331007 PK With/Without Coadministered Drug No Effect=1.00
Coadministered Drug | Dose of Coadministered Drug (mg) | Sofosbuvir Dose (mg) | N |  | Cmax | AUC | Cmin
Cyclosporine | 600 single dose | 400 single dose | 19 | sofosbuvir | 2.54 (1.87, 3.45) | 4.53 (3.26, 6.30) | NA
Cyclosporine | 600 single dose | 400 single dose | 19 | GS-331007 | 0.60 (0.53, 0.69) | 1.04 (0.90, 1.20) | NA
Darunavir (boosted with ritonavir) | 800/100 once daily | 400 single dose | 18 | sofosbuvir | 1.45 (1.10, 1.92) | 1.34 (1.12, 1.59) | NA
Darunavir (boosted with ritonavir) | 800/100 once daily | 400 single dose | 18 | GS-331007 | 0.97 (0.90, 1.05) | 1.24 (1.18, 1.30) | NA
Efavirenz [Administered as efavirenz/emtricitabine/tenofovir disoproxil fumarate fixed dose tablet] | 600 once daily | 400 single dose | 16 | sofosbuvir | 0.81 (0.60, 1.10) | 0.94 (0.76, 1.16) | NA
Emtricitabine | 200 once daily | 400 single dose | 16 | sofosbuvir | 0.81 (0.60, 1.10) | 0.94 (0.76, 1.16) | NA
Tenofovir disoproxil fumarate | 300 once daily | 400 single dose | 16 | GS-331007 | 0.77 (0.70, 0.84) | 0.84 (0.76, 0.92) | NA
Methadone | 30 to 130 once daily | 400 once daily | 14 | sofosbuvir | 0.95 [Comparison based on historic control] (0.68, 1.33) | 1.30 (1.00, 1.69) | NA
Methadone | 30 to 130 once daily | 400 once daily | 14 | GS-331007 | 0.73 (0.65, 0.83) | 1.04 (0.89, 1.22) | NA
Rilpivirine | 25 once daily | 400 single dose | 17 | sofosbuvir | 1.21 (0.90, 1.62) | 1.09 (0.94, 1.27) | NA
Rilpivirine | 25 once daily | 400 single dose | 17 | GS-331007 | 1.06 (0.99, 1.14) | 1.01 (0.97, 1.04) | NA
Tacrolimus | 5 single dose | 400 single dose | 16 | sofosbuvir | 0.97 (0.65, 1.43) | 1.13 (0.81, 1.57) | NA
Tacrolimus | 5 single dose | 400 single dose | 16 | GS-331007 | 0.97 (0.83, 1.14) | 1.00 (0.87, 1.13) | NA
NA = not available/not applicable

No effect on the pharmacokinetic parameters of sofosbuvir and GS-331007 was observed with raltegravir.

Table 10 Drug Interactions: Changes in Pharmacokinetic Parameters for Coadministered Drug in the Presence of Sofosbuvir [All interaction studies conducted in healthy volunteers]
Coadministered Drug | Dose of Coadministered Drug (mg) | Sofosbuvir Dose (mg) | N | Mean Ratio (90% CI) of Coadministered Drug PK With/Without Sofosbuvir No Effect=1.00
Coadministered Drug | Dose of Coadministered Drug (mg) | Sofosbuvir Dose (mg) | N | Cmax | AUC | Cmin
Norelgestromin | norgestimate 0.18/0.215/0.25/ ethinyl estradiol 0.025 once daily | 400 once daily | 15 | 1.07 (0.94, 1.22) | 1.06 (0.92, 1.21) | 1.07 (0.89, 1.28)
Norgestrel | norgestimate 0.18/0.215/0.25/ ethinyl estradiol 0.025 once daily | 400 once daily | 15 | 1.18 (0.99, 1.41) | 1.19 (0.98, 1.45) | 1.23 (1.00, 1.51)
Ethinyl estradiol | norgestimate 0.18/0.215/0.25/ ethinyl estradiol 0.025 once daily | 400 once daily | 15 | 1.15 (0.97, 1.36) | 1.09 (0.94, 1.26) | 0.99 (0.80, 1.23)
Raltegravir | 400 twice daily | 400 single dose | 19 | 0.57 (0.44, 0.75) | 0.73 (0.59, 0.91) | 0.95 (0.81, 1.12)
Tacrolimus | 5 single dose | 400 single dose | 16 | 0.73 (0.59, 0.90) | 1.09 (0.84, 1.40) | NA
Tenofovir disoproxil fumarate [Administered as efavirenz/emtricitabine/tenofovir disoproxil fumarate fixed dose tablet] | 300 once daily | 400 single dose | 16 | 1.25 (1.08, 1.45) | 0.98 (0.91, 1.05) | 0.99 (0.91, 1.07)
NA = not available/not applicable

No effect on the pharmacokinetic parameters of the following coadministered drugs was observed with sofosbuvir: cyclosporine, darunavir/ritonavir, efavirenz, emtricitabine, methadone, or rilpivirine.

12.4 Microbiology

Mechanism of Action

Sofosbuvir is an inhibitor of the HCV NS5B RNA-dependent RNA polymerase, which is essential for viral replication. Sofosbuvir is a nucleotide prodrug that undergoes intracellular metabolism to form the pharmacologically active uridine analog triphosphate (GS-461203), which can be incorporated into HCV RNA by the NS5B polymerase and acts as a chain terminator. In a biochemical assay, GS-461203 inhibited the polymerase activity of the recombinant NS5B from HCV genotype 1b, 2a, 3a and 4a with IC50 values ranging from 0.7 to 2.6 micromolar. GS-461203 is neither an inhibitor of human DNA and RNA polymerases nor an inhibitor of mitochondrial RNA polymerase.

Antiviral Activity

In HCV replicon assays, the EC50 values of sofosbuvir against full-length replicons from genotype 1a, 1b, 2a, 3a and 4a, and chimeric 1b replicons encoding NS5B from genotype 2b, 5a or 6a ranged from 0.014 to 0.11 micromolar. The median EC50 value of sofosbuvir against chimeric replicons encoding NS5B sequences from clinical isolates was 0.062 micromolar for genotype 1a (range 0.029–0.128 micromolar; N=67), 0.102 micromolar for genotype 1b (range 0.045–0.170 micromolar; N=29), 0.029 micromolar for genotype 2 (range 0.014–0.081 micromolar; N=15) and 0.081 micromolar for genotype 3a (range 0.024–0.181 micromolar; N=106). In infectious virus assays, the EC50 values of sofosbuvir against genotype 1a and 2a were 0.03 and 0.02 micromolar, respectively. The presence of 40% human serum had no effect on the anti-HCV activity of sofosbuvir. Evaluation of sofosbuvir in combination with interferon alpha or ribavirin showed no antagonistic effect in reducing HCV RNA levels in replicon cells.

Resistance

In Cell Culture

HCV replicons with reduced susceptibility to sofosbuvir have been selected in cell culture for multiple genotypes including 1b, 2a, 2b, 3a, 4a, 5a and 6a. Reduced susceptibility to sofosbuvir was associated with the primary NS5B substitution S282T in all replicon genotypes examined. An M289L substitution developed along with the S282T substitution in genotype 2a, 5 and 6 replicons. Site-directed mutagenesis of the S282T substitution in replicons of 8 genotypes conferred 2- to 18-fold reduced susceptibility to sofosbuvir and reduced the replication viral capacity by 89% to 99% compared to the corresponding wild-type. In biochemical assays, recombinant NS5B polymerase from genotypes 1b, 2a, 3a and 4a expressing the S282T substitution showed reduced susceptibility to GS-461203 compared to respective wild-types.

In Clinical Trials

In a pooled analysis of 982 subjects who received SOVALDI in Phase 3 trials, 224 subjects had post-baseline NS5B genotypic data from next generation nucleotide sequencing (assay cutoff of 1%).

Treatment-emergent substitutions L159F (n=6) and V321A (n=5) were detected in post-baseline samples from GT3a-infected subjects across the Phase 3 trials. No detectable shift in the phenotypic susceptibility to sofosbuvir of subject isolates with L159F or V321A substitutions was seen. The sofosbuvir-associated resistance substitution S282T was not detected at baseline or in the failure isolates from Phase 3 trials. However, an S282T substitution was detected in one genotype 2b subject who relapsed at Week 4 post-treatment after 12 weeks of sofosbuvir monotherapy in the Phase 2 trial P7977-0523 [ELECTRON]. The isolate from this subject displayed a mean 13.5-fold reduced susceptibility to sofosbuvir. For this subject, the S282T substitution was no longer detectable at Week 12 post-treatment by next generation sequencing with an assay cutoff of 1%.

In the trial done in subjects with hepatocellular carcinoma awaiting liver transplantation where subjects received up to 48 weeks of sofosbuvir and ribavirin, the L159F substitution emerged in multiple subjects with GT1a or GT2b HCV who experienced virologic failure (breakthrough and relapse). Furthermore, the presence of substitutions L159F and/or C316N at baseline was associated with sofosbuvir breakthrough and relapse post-transplant in multiple subjects infected with GT1b HCV. In addition, S282R and L320F substitutions were detected on-treatment by next generation sequencing in a subject infected with GT1a HCV with a partial treatment response.

The clinical significance of these substitutions is not known.

Cross Resistance

HCV replicons expressing the sofosbuvir-associated resistance substitution S282T were susceptible to NS5A inhibitors and ribavirin. HCV replicons expressing the ribavirin-associated substitutions T390I and F415Y were susceptible to sofosbuvir. Sofosbuvir was active against HCV replicons with NS3/4A protease inhibitor, NS5B non-nucleoside inhibitor and NS5A inhibitor resistant variants.

13 NONCLINICAL TOXICOLOGY

13.1 Carcinogenesis, Mutagenesis, Impairment of Fertility

Carcinogenesis and Mutagenesis

Use with Ribavirin and/or Peginterferon alfa: Refer to prescribing information for ribavirin and/or peginterferon alfa for information on carcinogenesis and mutagenesis.

Sofosbuvir was not genotoxic in a battery of in vitro or in vivo assays, including bacterial mutagenicity, chromosome aberration using human peripheral blood lymphocytes and in vivo mouse micronucleus assays.

Two-year carcinogenicity studies in mice and rats were conducted with sofosbuvir. Mice were administered doses of up to 200 mg/kg/day in males and 600 mg/kg/day in females, while rats were administered doses of up to 750 mg/kg/day in males and females. No increase in the incidence of drug-related neoplasms were observed at the highest doses tested in mice and rats, resulting in AUC exposure to the predominant circulating metabolite GS-331007 of approximately 7 and 30 times (in mice) and 13 and 17 times (in rats), in males and females respectively, the exposure in humans at the recommended clinical dose.

Impairment of Fertility

Use with Ribavirin and/or Peginterferon alfa: Refer to prescribing information for ribavirin and/or peginterferon alfa for information on impairment of fertility.

Sofosbuvir had no effects on embryo-fetal viability or on fertility when evaluated in rats. At the highest dose tested, AUC exposure to the predominant circulating metabolite GS-331007 was approximately 8 times the exposure in humans at the recommended clinical dose.

14 CLINICAL STUDIES

14.1 Description of Clinical Trials

The safety and efficacy of SOVALDI was evaluated in five Phase 3 trials in a total of 1724 HCV mono-infected subjects with genotypes 1 to 6 chronic hepatitis C virus, one Phase 3 trial in 223 HCV/HIV-1 coinfected subjects with genotype 1, 2 or 3 HCV, and one trial in 106 pediatric subjects 3 years of age and older with genotype 2 or 3 HCV, as summarized in Table 11 [see Clinical Studies (14.2, 14.3, 14.4, and 14.5)].

Table 11 Trials Conducted with SOVALDI with Peginterferon Alfa and/or Ribavirin in Subjects with Chronic HCV Genotype 1, 2, 3, or 4 Infection
Trial | Population | Study Arms (Number of Subjects Treated)
NEUTRINO [Open label.] (NCT01641640) | Treatment naïve (TN) (GT1, 4, 5 or 6) | SOVALDI+Peg-IFN alfa+RBV 12 weeks (327)
FISSION (NCT01497366) | TN (GT2 or 3) | SOVALDI+RBV 12 Weeks (256) Peg-IFN alfa+RBV 24 weeks (243)
POSITRON [Double-blind, placebo-controlled.] (NCT01542788) | Interferon intolerant, ineligible or unwilling subjects (GT2 or 3) | SOVALDI+RBV 12 Weeks (207) Placebo 12 weeks (71)
FUSION (NCT01604850) | Previous interferon relapsers or nonresponders (GT2 or 3) | SOVALDI+RBV 12 Weeks (103) SOVALDI+RBV 16 Weeks (98)
VALENCE (NCT01682720) | TN or previous interferon relapsers or nonresponders (GT2 or 3) | SOVALDI+RBV 12 Weeks for GT2 (73) SOVALDI+RBV 12 Weeks for GT3 (11) SOVALDI+RBV 24 Weeks for GT3 (250) Placebo for 12 weeks (85)
PHOTON-1 (NCT01667731) | - HCV/HIV-1 coinfected TN (GT1) - HCV/HIV-1 coinfected TN or previous interferon relapsers or nonresponders (GT2 or 3) | SOVALDI+RBV 24 Weeks for GT1 (114) SOVALDI+RBV 12 Weeks for GT2 or 3 TN (68) SOVALDI+RBV 24 Weeks for GT2 or 3 previous interferon relapsers or nonresponders (41)
1112 (NCT02175758) | GT2 or GT3 pediatric subjects 3 years of age and older | SOVALDI+RBV 12 Weeks for GT2 (31) SOVALDI+RBV 24 Weeks for GT3 (75)

Subjects in the adult trials did not have cirrhosis or had compensated cirrhosis. SOVALDI was administered at a dose of 400 mg once daily. The ribavirin (RBV) dosage for adult subjects was weight-based at 1000–1200 mg daily administered in two divided doses when used in combination with SOVALDI, and the peginterferon alfa 2a dosage, where applicable, was 180 micrograms per week. Treatment duration was fixed in each trial and was not guided by subjects' HCV RNA levels (no response guided algorithm). Plasma HCV RNA values were measured during the clinical trials using the COBAS TaqMan HCV test (version 2.0), for use with the High Pure System. The assay had a lower limit of quantification (LLOQ) of 25 IU per mL. Sustained virologic response (SVR12) was the primary endpoint which was defined as HCV RNA less than LLOQ at 12 weeks after the end of treatment.

14.2 Clinical Trials in Subjects with Genotype 1 or 4 HCV

Treatment-Naïve Adults ─ NEUTRINO (Study 110)

NEUTRINO was an open-label, single-arm trial that evaluated 12 weeks of treatment with SOVALDI in combination with peginterferon alfa 2a and ribavirin in treatment-naïve subjects with genotype 1, 4, 5 or 6 HCV infection compared to pre-specified historical control.

Treated subjects (N=327) had a median age of 54 years (range: 19 to 70); 64% of the subjects were male; 79% were White, 17% were Black; 14% were Hispanic or Latino; mean body mass index was 29 kg/m^2 (range: 18 to 56 kg/m^2); 78% had baseline HCV RNA greater than 6 log10 IU per mL; 17% had cirrhosis; 89% had HCV genotype 1; 9% had HCV genotype 4 and 2% had HCV genotype 5 or 6. Table 12 presents the SVR12 for the treatment group of SOVALDI + peginterferon alfa + ribavirin in subjects with genotype 1 or 4 HCV. Available data on subjects with genotype 5 or 6 HCV treated with SOVALDI + peginterferon alfa + ribavirin for 12 weeks were insufficient for dosing recommendations; therefore these results are not presented in Table 12 [see Use in Specific Populations (8.10)].

Table 12 Study NEUTRINO: SVR12 for Treatment-Naïve Subjects with Genotype 1 or 4 HCV
 | SOVALDI + Peg-IFN alfa + RBV 12 weeks
 | N=320
Overall SVR | 90% (289/320)
Genotype 1 [One subject had genotype 1a/1b mixed infection.] | 90% (262/292)
Genotype 1a | 92% (206/225)
Genotype 1b | 83% (55/66)
Genotype 4 | 96% (27/28)
Outcome for subjects without SVR
On-treatment virologic failure | 0/320
Relapse [The denominator for relapse is the number of subjects with HCV RNA <LLOQ at their last on-treatment assessment.] | 9% (28/319)
Other [Other includes subjects who did not achieve SVR and did not meet virologic failure criteria (e.g., lost to follow-up).] | 1% (3/320)

SVR12 for selected subgroups are presented in Table 13.

Table 13 SVR12 Rates for Selected Subgroups in NEUTRINO in Subjects with Genotype 1 or 4 HCV
 | SOVALDI + Peg-IFN alfa + RBV 12 weeks
Cirrhosis
No | 93% (247/267)
Yes | 79% (42/53)
Race
Black | 87% (47/54)
Non-black | 91% (242/266)
Multiple Baseline Factors
Genotype 1, Metavir F3/F4 fibrosis, IL28B non-C/C, HCV RNA >800,000 IU/mL | 71% (37/52)

SVR12 rates were 99% (89/90) in subjects with genotype 1 or 4 HCV and baseline IL28B C/C allele and 87% (200/230) in subjects with genotype 1 or 4 HCV and baseline IL28B non-C/C alleles.

It is estimated that the SVR12 in patients who previously failed pegylated interferon and ribavirin therapy will approximate the observed SVR12 in NEUTRINO subjects with multiple baseline factors traditionally associated with a lower response to interferon-based treatment (Table 13).

The SVR12 rate in the NEUTRINO trial in genotype 1 subjects with IL28B non-C/C alleles, HCV RNA greater than 800,000 IU/mL and Metavir F3/F4 fibrosis was 71% (37/52).

14.3 Clinical Trials in Subjects with Genotype 2 or 3 HCV

Treatment-Naïve Adults ─ FISSION (Study 1231)

FISSION was a randomized, open-label, active-controlled trial that evaluated 12 weeks of treatment with SOVALDI and ribavirin compared to 24 weeks of treatment with peginterferon alfa 2a and ribavirin in treatment-naïve subjects with genotype 2 and 3 HCV. The ribavirin dosage used in the SOVALDI + ribavirin and peginterferon alfa 2a + ribavirin arms were weight-based 1000–1200 mg per day and 800 mg per day regardless of weight, respectively. Subjects were randomized in a 1:1 ratio and stratified by cirrhosis (presence vs. absence), HCV genotype (2 vs. 3) and baseline HCV RNA level (less than 6 log10 IU/mL vs. at least 6 log10 IU/mL). Subjects with genotype 2 or 3 HCV were enrolled in an approximately 1:3 ratio.

Treated subjects (N=499) had a median age of 50 years (range: 19 to 77); 66% of the subjects were male; 87% were White, 3% were Black; 14% were Hispanic or Latino; mean body mass index was 28 kg/m^2 (range: 17 to 52 kg/m^2); 57% had baseline HCV RNA levels greater than 6 log10 IU per mL; 20% had cirrhosis; 72% had HCV genotype 3. Table 14 presents the SVR12 for the treatment groups of SOVALDI + ribavirin and peginterferon alfa + ribavirin in subjects with genotype 2 HCV. SVR12 for genotype 3 subjects treated with SOVALDI + ribavirin for 12 weeks was suboptimal; therefore these results are not presented in Table 14.

Table 14 Study FISSION: SVR12 in Treatment-Naïve Subjects with Genotype 2 HCV
 | SOVALDI + RBV 12 weeks | Peg-IFN alfa + RBV 24 weeks
 | N=73 [Including three subjects with recombinant genotype 2/1 HCV infection.] | N=67
SVR12 | 95% (69/73) | 78% (52/67)
Outcome for subjects without SVR12
On-treatment virologic failure | 0/73 | 4% (3/67)
Relapse [The denominator for relapse is the number of subjects with HCV RNA <LLOQ at their last on-treatment assessment.] | 5% (4/73) | 15% (9/62)
Other [Other includes subjects who did not achieve SVR and did not meet virologic failure criteria (e.g., lost to follow-up).] | 0/73 | 4% (3/67)

SVR12 for genotype 2 HCV-infected subjects with cirrhosis at baseline are presented in Table 15.

Table 15 SVR12 Rates by Cirrhosis in Study FISSION in Subjects with Genotype 2 HCV
 | SOVALDI + RBV 12 weeks | Peg-IFN alfa + RBV 24 weeks
 | N=73 | N=67
Cirrhosis
No | 97% (59/61) | 81% (44/54)
Yes | 83% (10/12) | 62% (8/13)

Interferon Intolerant, Ineligible or Unwilling Adults ─ POSITRON (Study 0107)

POSITRON was a randomized, double-blinded, placebo-controlled trial that evaluated 12 weeks of treatment with SOVALDI and ribavirin (N=207) compared to placebo (N=71) in subjects who are interferon intolerant, ineligible or unwilling. Subjects were randomized in 3:1 ratio and stratified by cirrhosis (presence vs. absence).

Treated subjects (N=278) had a median age of 54 years (range: 21 to 75); 54% of the subjects were male; 91% were White, 5% were Black; 11% were Hispanic or Latino; mean body mass index was 28 kg/m^2 (range: 18 to 53 kg/m^2); 70% had baseline HCV RNA levels greater than 6 log10 IU per mL; 16% had cirrhosis; 49% had HCV genotype 3. The proportions of subjects who were interferon intolerant, ineligible, or unwilling were 9%, 44%, and 47%, respectively. Most subjects had no prior HCV treatment (81%). Table 16 presents the SVR12 for the treatment groups of SOVALDI + ribavirin and placebo in subjects with genotype 2 HCV. SVR12 for genotype 3 subjects treated with SOVALDI + ribavirin for 12 weeks was suboptimal; therefore these results are not presented in Table 16.

Table 16 Study POSITRON: SVR12 in Interferon Intolerant, Ineligible or Unwilling Subjects with Genotype 2 HCV
 | SOVALDI + RBV 12 weeks | Placebo 12 weeks
 | N=109 | N= 34
SVR12 | 93% (101/109) | 0/34
Outcome for subjects without SVR12
On-treatment virologic failure | 0/109 | 97% (33/34)
Relapse [The denominator for relapse is the number of subjects with HCV RNA <LLOQ at their last on-treatment assessment.] | 5% (5/107) | 0/0
Other [Other includes subjects who did not achieve SVR and did not meet virologic failure criteria (e.g., lost to follow-up).] | 3% (3/109) | 3% (1/34)

Table 17 presents the subgroup analysis for cirrhosis and interferon classification in subjects with genotype 2 HCV.

Table 17 SVR12 Rates for Selected Subgroups in POSITRON in Subjects with Genotype 2 HCV
 | SOVALDI + RBV 12 weeks
 | N=109
Cirrhosis
No | 92% (85/92)
Yes | 94% (16/17)
Interferon Classification
Ineligible | 88% (36/41)
Intolerant | 100% (9/9)
Unwilling | 95% (56/59)

Previously Treated Adults ─ FUSION (Study 0108)

FUSION was a randomized, double-blinded trial that evaluated 12 or 16 weeks of treatment with SOVALDI and ribavirin in subjects who did not achieve SVR with prior interferon-based treatment (relapsers and nonresponders). Subjects were randomized in a 1:1 ratio and stratified by cirrhosis (presence vs. absence) and HCV genotype (2 vs. 3).

Treated subjects (N=201) had a median age of 56 years (range: 24 to 70); 70% of the subjects were male; 87% were White; 3% were Black; 9% were Hispanic or Latino; mean body mass index was 29 kg/m^2 (range: 19 to 44 kg/m^2); 73% had baseline HCV RNA levels greater than 6 log10 IU per mL; 34% had cirrhosis; 63% had HCV genotype 3; 75% were prior relapsers. Table 18 presents the SVR12 for the treatment groups of SOVALDI + ribavirin for 12 weeks in subjects with genotype 2 HCV. Treatment of 16 weeks in subjects with genotype 2 HCV was not shown to increase the SVR12 observed with 12 weeks of treatment. SVR12 for genotype 3 subjects treated with SOVALDI + ribavirin for 12 or 16 weeks was suboptimal; therefore these results are not presented in Table 18.

Table 18 Study FUSION: SVR12 in Previous Interferon Relapsers and Nonresponders with Genotype 2 HCV
 | SOVALDI + RBV 12 weeks
 | N=39 [Including three subjects with recombinant genotype 2/1 HCV infection.]
SVR12 | 82% (32/39)
Outcome for subjects without SVR12
On-treatment virologic failure | 0/39
Relapse [The denominator for relapse is the number of subjects with HCV RNA <LLOQ at their last on-treatment assessment.] | 18% (7/39)
Other [Other includes subjects who did not achieve SVR and did not meet virologic failure criteria (e.g., lost to follow-up).] | 0/39

Table 19 presents the subgroup analysis for cirrhosis and response to prior HCV treatment in subjects with genotype 2 HCV.

Table 19 SVR12 Rates for Selected Subgroups in Study FUSION in Subjects with Genotype 2 HCV
 | SOVALDI + RBV 12 weeks
 | N=39
Cirrhosis
No | 90% (26/29)
Yes | 60% (6/10)
Response to prior HCV treatment
Relapser/ breakthrough | 86% (25/29)
Nonresponder | 70% (7/10)

Treatment-Naïve and Previously Treated Adults ─ VALENCE (Study 0133)

The VALENCE trial evaluated SOVALDI in combination with weight-based ribavirin for the treatment of genotype 2 or 3 HCV infection in treatment-naïve subjects or subjects who did not achieve SVR with prior interferon-based treatment, including subjects with compensated cirrhosis. The original trial design was a 4 to 1 randomization to SOVALDI + ribavirin for 12 weeks or placebo. Based on emerging data, this trial was unblinded and all genotype 2 HCV-infected subjects continued the original planned treatment and received SOVALDI + ribavirin for 12 weeks, and duration of treatment with SOVALDI + ribavirin in genotype 3 HCV-infected subjects was extended to 24 weeks. Eleven genotype 3 subjects had already completed SOVALDI + ribavirin for 12 weeks at the time of the amendment.

Treated subjects (N=419) had a median age of 51 years (range: 19 to 74); 60% of the subjects were male; mean body mass index was 26 kg/m^2 (range: 17 to 44 kg/m^2); the mean baseline HCV RNA level was 6.4 log10 IU per mL; 78% had HCV genotype 3; 58% of the subjects were treatment-experienced and 65% of those subjects experienced relapse/breakthrough to prior HCV treatment.

Table 20 presents the SVR12 for the treatment groups of SOVALDI + ribavirin for 12 weeks and 24 weeks.

Table 20 Study VALENCE [Placebo subjects (N=85) were not included as none achieved SVR12.] : SVR12 in Subjects with Genotype 2 or 3 HCV Who were Treatment-Naïve or Who Did Not Achieve SVR12 with Prior Interferon-Based Treatment
 | Genotype 2 SOVALDI + RBV 12 weeks | Genotype 3 SOVALDI + RBV 24 weeks
 | N=73 | N=250
Overall SVR | 93% (68/73) | 84% (210/250)
Outcome for subjects without SVR
On-treatment virologic failure | 0% (0/73) | <1% (1/250)
Relapse [The denominator for relapse is the number of subjects with HCV RNA <LLOQ at their last on-treatment assessment.] | 7% (5/73) | 14% (34/249)
Treatment-naïve | 3% (1/32) | 5% (5/105)
Treatment-experienced | 10% (4/41) | 20% (29/144)
Other [Other includes subjects who did not achieve SVR12 and did not meet virologic failure criteria (e.g., lost to follow-up).] | 0% (0/73) | 2% (5/250)

Table 21 presents the subgroup analysis by genotype for cirrhosis and prior HCV treatment experience.

Table 21 SVR12 Rates for Selected Subgroups by Genotype in Study VALENCE in Subjects with Genotype 2 or 3 HCV
 | Genotype 2 SOVALDI + RBV 12 weeks | Genotype 3 SOVALDI + RBV 24 weeks
 | N=73 | N=250
Treatment-naïve | 97% (31/32) | 93% (98/105)
Non-cirrhotic | 97% (29/30) | 93% (86/92)
Cirrhotic | 100% (2/2) | 92% (12/13)
Treatment-experienced | 90% (37/41) | 77% (112/145)
Non-cirrhotic | 91% (30/33) | 85% (85/100)
Cirrhotic | 88% (7/8) | 60% (27/45)

14.4 Clinical Trials in Adult Subjects Coinfected with HCV and HIV-1 ─ Photon-1 (Study 0123)

SOVALDI was studied in an open-label clinical trial (Study PHOTON-1) evaluating the safety and efficacy of 12 or 24 weeks of treatment with SOVALDI and ribavirin in adult subjects with genotype 1, 2 or 3 chronic hepatitis C coinfected with HIV-1. Genotype 2 and 3 subjects were either HCV treatment-naïve or experienced, whereas genotype 1 subjects were all treatment-naïve. Subjects received 400 mg SOVALDI and weight-based ribavirin (1000 mg for subjects weighing less than 75 kg or 1200 mg for subjects weighing at least 75 kg) daily for 12 or 24 weeks based on genotype and prior treatment history. Subjects were either not on antiretroviral therapy with a CD4+ cell count greater than 500 cells/mm^3 or had virologically suppressed HIV-1 with a CD4+ cell count greater than 200 cells/mm^3. Efficacy data 12 weeks post treatment are available for 210 subjects (see Table 22).

Table 22 Study PHOTON-1 [Subjects with genotype 2 HCV treated with SOVALDI + RBV for 24 weeks (N=15) and subjects with genotype 3 HCV treated with SOVALDI + RBV for 12 weeks (N=42) are not included in the table.] : SVR12 in Treatment-Naïve or Treatment-Experienced Subjects with Genotype 1, 2, or 3 HCV
 | HCV genotype 1 | HCV genotype 2 | HCV genotype 3
 | SOVALDI + RBV 24 weeks TN (N=114) | SOVALDI + RBV 12 weeks TN (N=26) | SOVALDI + RBV 24 weeks TE (N=13)
Overall | 76% (87/114) | 88% (23/26) | 92% (12/13)
Outcome for subjects without SVR12
On-treatment virologic failure | 1% (1/114) | 4% (1/26) | 0/13
Relapse [The denominator for relapse is the number of subjects with HCV RNA <LLOQ at their last on-treatment assessment.] | 22% (25/113) | 0/25 | 8% (1/13)
Other [Other includes subjects who did not achieve SVR12 and did not meet virologic failure criteria (e.g., lost to follow-up).] | 1% (1/114) | 8% (2/26) | 0/13
TN = Treatment-naïve; TE = Treatment-experienced

In subjects with HCV genotype 1 infection, the SVR12 rate was 82% (74/90) in subjects with genotype 1a infection and 54% (13/24) in subjects with genotype 1b infection, with relapse accounting for the majority of treatment failures. SVR12 rates in subjects with HCV genotype 1 infection were 80% (24/30) in subjects with baseline IL28B C/C allele and 75% (62/83) in subjects with baseline IL28B non-C/C alleles.

In the 223 HCV subjects with HIV-1 coinfection, the percentage of CD4+ cells did not change during treatment. Median CD4+ cell count decreases of 85 cells/mm^3 and 84 cells/mm^3 were observed at the end of treatment with SOVALDI + ribavirin for 12 or 24 weeks, respectively. HIV-1 rebound during SOVALDI + ribavirin treatment occurred in 2 subjects (0.9%) on antiretroviral therapy.

14.5 Clinical Trial in Pediatrics (Study 1112)

The efficacy of SOVALDI in HCV-infected pediatric subjects 3 years of age and older was evaluated in 106 subjects with HCV genotype 2 (N = 31) or genotype 3 (N = 75) in a Phase 2, open label clinical trial. Subjects with HCV genotype 2 or 3 infection in the trial were treated with SOVALDI and weight-based ribavirin for 12 or 24 weeks, respectively [see Dosage and Administration (2.3)].

Subjects 12 Years to <18 Years of Age: SOVALDI was evaluated in 52 subjects12 years to <18 years of age with HCV genotype 2 (N = 13) or genotype 3 (N = 39) infection. The median age was 15 years (range: 12 to 17); 40% of the subjects were female; 90% were White, 4% were Black, and 2% were Asian; 4% were Hispanic/Latino; mean body mass index was 22 kg/m^2 (range: 16 to 32 kg/m^2);mean weight was 60 kg (range: 30 to 101 kg); 17% were treatment experienced; 65% had baseline HCV RNA levels greater than or equal to 800,000 IU/mL; and no subjects had known cirrhosis. The majority of subjects (71%) had been infected through vertical transmission.

The SVR12 rate was 100% [13/13] in genotype 2 subjects and 97% [38/39] in genotype 3 subjects. No subject experienced on-treatment virologic failure or relapse.

Subjects 6 Years to <12 Years of Age: SOVALDI was evaluated in 41 subjects 6 years to <12 years of age with HCV genotype 2 (N = 13) or genotype 3 (N = 28) infection. The median age was 9 years (range: 6 to 11); 73% of the subjects were female; 71% were White and 20% were Asian; 15% were Hispanic/Latino; mean body mass index was 19 kg/m^2 (range: 13 to 32 kg/m^2); mean weight was 34 kg (range 15 to 80 kg); 98% were treatment naive; 46% had baseline HCV RNA levels greater than or equal to 800,000 IU/mL; and no subjects had known cirrhosis. The majority of subjects (98%) had been infected through vertical transmission.

The SVR12 rate was 100% (13/13) in genotype 2 and 100% (28/28) in genotype 3 subjects.). No subjects experienced on-treatment virologic failure or relapse.

Subjects 3 Years to <6 Years of Age: SOVALDI was evaluated in 13 subjects 3 years to <6 years of age with HCV genotype 2 (N = 5) or genotype 3 (N = 8) infection. The median age was 4 years (range: 3 to 5); 77% of the subjects were female; 69% were White, 8% were Black, and 8% were Asian; 8% were Hispanic/Latino; mean body mass index was 15 kg/m^2 (range: 13 to 17 kg/m^2); mean weight was 17 kg (range 13 to 19 kg); 100% were treatment naive; 23% had baseline HCV RNA levels greater than or equal to 800,000 IU/mL; and no subjects had known cirrhosis. The majority of subjects (85%) had been infected through vertical transmission.

The SVR12 rate was 80% (4/5) in genotype 2 subjects and 100% (8/8) in genotype 3 subjects. No subjects experienced on-treatment virologic failure or relapse. One subject prematurely discontinued study treatment due to an adverse event.

16 HOW SUPPLIED/STORAGE AND HANDLING

Tablets

SOVALDI tablets, 400 mg, are yellow, capsule-shaped, film-coated tablets containing 400 mg sofosbuvir debossed with "GSI" on one side and "7977" on the other side. Each bottle contains 28 tablets (NDC 61958-1501-1), a silica gel desiccant and polyester coil with a child-resistant closure.

SOVALDI tablets, 200 mg, are yellow, oval-shaped, film-coated tablets containing 200 mg sofosbuvir debossed with "GSI" on one side and "200" on the other side. Each bottle contains 28 tablets (NDC 61958-1503-1) and a polyester coil with a child-resistant closure.

STORAGE AND HANDLING

Store below 30 °C (86 °F).

- Dispense only in original container
- Do not use if seal over bottle opening is broken or missing

Oral Pellets

SOVALDI pellets, 150 mg, are white to off-white pellets supplied as unit-dose packets in cartons. Each carton contains 28 packets (NDC 61958-1504-1)

SOVALDI pellets, 200 mg, are white to off-white pellets supplied as unit-dose packets in cartons. Each carton contains 28 packets (NDC 61958-1505-1)

- Store below 30 °C (86 °F).
- Do not use if carton tamper-evident or packet seal is broken or damaged.

17 PATIENT COUNSELING INFORMATION

Advise the patient to read the FDA-approved patient labeling (Patient Information and Instructions for Use).

Risk of Hepatitis B Virus Reactivation in Patients Coinfected with HCV and HBV

Inform patients that HBV reactivation can occur in patients coinfected with HBV during or after treatment of HCV infection. Advise patients to tell their healthcare provider if they have a history of HBV infection [see Warnings and Precautions (5.1)].

Serious Symptomatic Bradycardia When Coadministered with Amiodarone

Advise patients to seek medical evaluation immediately for symptoms of bradycardia such as near-fainting or fainting, dizziness or lightheadedness, malaise, weakness, excessive tiredness, shortness of breath, chest pain, confusion or memory problems [see Warnings and Precautions (5.2), Adverse Reactions (6.2), and Drug Interactions (7.1)].

Pregnancy

Advise patients to avoid pregnancy during combination treatment with SOVALDI and ribavirin or SOVALDI and peginterferon and ribavirin. Inform patients to notify their health care provider immediately in the event of a pregnancy [see Use in Specific Populations (8.1)].

Drug Interactions

Advise patients that SOVALDI may interact with some drugs; therefore, patients should be advised to report the use of any prescription, non-prescription medication or herbal products to their healthcare provider [see Warnings and Precautions (5.3) and Drug Interactions (7.1)].

Hepatitis C Virus Transmission

Inform patients that the effect of treatment of hepatitis C infection on transmission is not known, and that appropriate precautions to prevent transmission of the hepatitis C virus during treatment or in the event of treatment failure should be taken.

Administration

Advise patients to take SOVALDI every day at the regularly scheduled time with or without food. Inform patients that it is important not to miss or skip doses and to take SOVALDI for the duration that is recommended by the physician.

For SOVALDI oral pellets, advise patients or caregivers to read and follow the Instructions for Use for preparing the correct dose.

Important Information on Coadministration with Ribavirin or Peginterferon and Ribavirin

Advise patients that the recommended regimen for patients with genotype 1 or 4 HCV infection is SOVALDI administered in combination with peginterferon alfa and ribavirin and the recommended regimen for patients with genotype 2 or 3 HCV infection is SOVALDI administered in combination with ribavirin. If peginterferon and/or ribavirin are permanently discontinued, SOVALDI should also be discontinued.

Manufactured and distributed by:
Gilead Sciences, Inc.
Foster City, CA 94404

SOVALDI and HARVONI are trademarks of Gilead Sciences, Inc., or its related companies. All other trademarks referenced herein are the property of their respective owners.

©2024 Gilead Sciences, Inc. All rights reserved.

204671-GS-0011

Patient Information

SOVALDI® (soh-VAHL-dee)
(sofosbuvir)
tablets

SOVALDI® (soh-VAHL-dee)
(sofosbuvir)
oral pellets

Important: SOVALDI is used in combination with other antiviral medicines. When taking SOVALDI with ribavirin or in combination with peginterferon alfa and ribavirin you should also read those Medication Guides. The information in this Patient Information Leaflet talks about SOVALDI when it is used with ribavirin and in combination with peginterferon alfa and ribavirin.

What is the most important information I should know about SOVALDI?
SOVALDI can cause serious side effects, including:

- Hepatitis B virus reactivation: Before starting treatment with SOVALDI, your healthcare provider will do blood tests to check for hepatitis B virus infection. If you have ever had hepatitis B virus infection, the hepatitis B virus could become active again during or after treatment of hepatitis C virus with SOVALDI. Hepatitis B virus becoming active again (called reactivation) may cause serious liver problems including liver failure and death. Your healthcare provider will monitor you if you are at risk for hepatitis B virus reactivation during treatment and after you stop taking SOVALDI.

For more information about side effects, see the section "What are the possible side effects of SOVALDI?"

What is SOVALDI?
SOVALDI is a prescription medicine used with other antiviral medicines to treat adults with chronic (lasting a long time) hepatitis C virus (HCV):

- genotype 1 or 4 infection without cirrhosis or with compensated cirrhosis in combination with peginterferon alfa and ribavirin
- genotype 2 or 3 infection without cirrhosis or with compensated cirrhosis in combination with ribavirin

SOVALDI is used to treat children 3 years of age and older with chronic HCV genotype 2 or 3 infection without cirrhosis or with compensated cirrhosis in combination with ribavirin.
It is not known if SOVALDI is safe and effective in children under 3 years of age with HCV genotype 2 or 3 infection, or with HCV genotype 1 or 4 infection.
It is not known if SOVALDI is safe and effective in people who have had a liver transplant.

Before taking SOVALDI, tell your healthcare provider about all of your medical conditions, including if you:

- have ever had hepatitis B virus infection
- have liver problems other than hepatitis C infection
- have had a liver transplant
- have severe kidney problems or you are on dialysis
- have HIV infection
- are pregnant or plan to become pregnant. It is not known if SOVALDI will harm your unborn baby.
  - Males and females who take SOVALDI in combination with ribavirin should also read the ribavirin Medication Guide for important pregnancy, contraception, and infertility information.
- are breastfeeding or plan to breastfeed. It is not known if SOVALDI passes into your breast milk. Talk to your healthcare provider about the best way to feed your baby during treatment with SOVALDI.

Tell your healthcare provider about all the medicines you take, including prescription and over-the-counter medicines, vitamins, and herbal supplements. SOVALDI and other medicines may affect each other. This can cause you to have too much or not enough SOVALDI or other medicines in your body. This may affect the way SOVALDI or your other medicines work, or may cause side effects.
Keep a list of your medicines to show your healthcare provider and pharmacist.

- You can ask your healthcare provider or pharmacist for a list of medicines that interact with SOVALDI.
- Do not start taking a new medicine without telling your healthcare provider. Your healthcare provider can tell you if it is safe to take SOVALDI with other medicines.

How should I take SOVALDI?

- Take SOVALDI exactly as your healthcare provider tells you to take it. Do not change your dose unless your healthcare provider tells you to.
- Do not stop taking SOVALDI without first talking with your healthcare provider.
- Take SOVALDI tablets or oral pellets by mouth, with or without food.
- For adults the usual dose of SOVALDI is one 400 mg tablet each day.
- For children 3 years of age and older, your healthcare provider will prescribe the right dose of SOVALDI tablets or oral pellets based on your child's body weight.
  - Tell your healthcare provider if your child has problems with swallowing tablets.
  - If your healthcare provider prescribes SOVALDI pellets for your child, see "How should I give SOVALDI oral pellets to my child."
- Do not miss a dose of SOVALDI. Missing a dose lowers the amount of medicine in your blood. Refill your SOVALDI prescription before you run out of medicine.
- If you take too much SOVALDI, call your healthcare provider or go to the nearest hospital emergency room right away.

How should I give SOVALDI oral pellets to my child?
See the detailed Instructions for Use for information about how to give or take a dose of SOVALDI oral pellets.

- Administer SOVALDI oral pellets exactly as instructed by your healthcare provider.
- Do not open the packet until ready to use.
- Hold the SOVALDI pellets packet with the cut line on top.
- Shake the SOVALDI pellets packet gently to settle the pellets.
- Tear or cut the SOVALDI packet along the cut line.
- SOVALDI pellets can be taken right in the mouth without chewing, or with food.
- If SOVALDI pellets are taken with food, sprinkle the pellets on one or more spoonfuls of non-acidic soft food at or below room temperature. Examples of non-acidic foods include pudding, chocolate syrup, mashed potato, and ice cream. Take SOVALDI pellets within 30 minutes of gently mixing with food and swallow the entire contents without chewing to avoid a bitter taste.
- Do not store any leftover SOVALDI mixture (oral pellets mixed with food) for use at a later time. Throw away any unused portion.

What are the possible side effects of SOVALDI?
SOVALDI can cause serious side effects, including:

- Hepatitis B virus reactivation. See "What is the most important information I should know about SOVALDI?"
- Slow heart rate (bradycardia). SOVALDI treatment may result in slowing of the heart rate along with other symptoms when taken with amiodarone (Cordarone®, Nexterone®, Pacerone®), a medicine used to treat certain heart problems. In some cases bradycardia has led to death or the need for a heart pacemaker when amiodarone is taken with SOVALDI. Get medical help right away if you take amiodarone with SOVALDI and get any of the following symptoms:

- fainting or near-fainting
- dizziness or lightheadedness
- not feeling well

- weakness
- extreme tiredness
- shortness of breath

- chest pain
- confusion
- memory problems

The most common side effects of SOVALDI when used in combination with ribavirin include:

- tiredness

- headache

The most common side effects of SOVALDI when used in combination with peginterferon alfa and ribavirin include:

- tiredness
- headache

- nausea
- difficulty sleeping

- low red blood cell count

These are not all the possible side effects of SOVALDI. For more information, ask your healthcare provider or pharmacist.
Call your doctor for medical advice about side effects. You may report side effects to FDA at 1-800-FDA-1088.

How should I store SOVALDI?

- Store SOVALDI tablets or pellets below 86°F (30°C).
- Keep SOVALDI tablets in the original container.
- Do not use SOVALDI tablets if the seal over the bottle opening is broken or missing.
- Do not use SOVALDI pellets if the carton tamper-evident seal, or the pellets packet seal, is broken or damaged.

Keep SOVALDI and all medicines out of the reach of children.

General information about the safe and effective use of SOVALDI.
Medicines are sometimes prescribed for purposes other than those listed in a Patient Information leaflet. Do not use SOVALDI for a condition for which it was not prescribed. Do not give SOVALDI to other people, even if they have the same symptoms you have. It may harm them. You can ask your healthcare provider or pharmacist for information about SOVALDI that is written for health professionals. For more information, call 1-800-445-3235 or go to www.SOVALDI.com.

What are the ingredients in SOVALDI?
Active ingredient: sofosbuvir
Inactive ingredients, Tablets: colloidal silicon dioxide, croscarmellose sodium, magnesium stearate, mannitol, and microcrystalline cellulose. The tablet film-coat contains polyethylene glycol, polyvinyl alcohol, talc, titanium dioxide, and yellow iron oxide.
Inactive ingredients, Oral Pellets: amino methacrylate copolymer, colloidal silicon dioxide, croscarmellose sodium, hydroxypropyl cellulose, hypromellose, lactose monohydrate, microcrystalline cellulose, polyethylene glycol, silicon dioxide, sodium lauryl sulfate, sodium stearyl fumarate, stearic acid, and talc.
Gilead Sciences, Inc., Foster City, CA 94404
For more information, call 1-800-445-3235 or go to www.SOVALDI.com.
SOVALDI is a trademark of Gilead Sciences, Inc., or its related companies. All other trademarks referenced herein are the property of their respective owners.
©2024 Gilead Sciences, Inc. All rights reserved.
204671-GS-011

This Patient Information has been approved by the U.S. Food and Drug Administration.

Revised: 03/2020

INSTRUCTIONS FOR USE

SOVALDI® (soh-VAHL-dee)
(sofosbuvir)
pellets, for oral use

Read the Patient Information that comes with SOVALDI oral pellets for important information about SOVALDI.

This Instructions for Use contains information on how to take SOVALDI oral pellets. Be sure you understand and follow the instructions. If you have any questions, ask your healthcare provider or pharmacist.

Important Information You Need to Know Before Taking SOVALDI oral pellets

- For oral use only (take by mouth with or without food).
- Do not open the SOVALDI oral pellet packet(s) until ready to use.
- SOVALDI oral pellets are white to off-white pellets supplied as single-use packets in cartons. Each carton contains 28 packets.
- Do not use SOVALDI oral pellets if the carton tamper-evident seal, or the pellets packet seal, is broken or damaged.

Preparing a dose of SOVALDI oral pellets to be taken with food:

Before you prepare a dose of SOVALDI oral pellets to be taken with food, gather the following supplies:

- Daily SOVALDI oral pellet packet(s), as prescribed by your healthcare provider
- One or more spoonfuls of non-acidic soft food such as pudding, chocolate syrup, mashed potato, or ice cream
- Bowl
- Spoon
- Scissors (optional)

Step 1: Add one or more spoonfuls of non-acidic soft food to the bowl first.

Step 2: Hold the SOVALDI oral pellets packet with the cut line on top (see Figure A).

Step 3: Shake the packet gently to settle the pellets to the bottom of the packet (see Figure B).

Figure A

Figure B

Step 4: Cut the packet along the cut line with scissors (see Figure C), or fold the packet back at the tear line (see Figure D) and tear open (see Figure E).

Figure C

Figure D

Figure E

Step 5: Carefully pour the entire contents of the prescribed number of SOVALDI oral pellet packet(s) onto the food in the bowl and gently mix with a spoon (see Figure F). Make sure that no SOVALDI oral pellets remain in the packet(s).

Figure F

Step 6: Take the SOVALDI oral pellets and food mixture within 30 minutes without chewing to avoid a bitter taste. Ensure all of the SOVALDI oral pellets are taken.

Preparing a dose of SOVALDI oral pellets to be taken without food:

Before you prepare a dose of SOVALDI oral pellets to be taken without food, gather the following supplies:

- Daily SOVALDI oral pellet packet(s), as prescribed by your healthcare provider
- Scissors (optional)
- Water (optional)

Step 1: Hold the SOVALDI oral pellets packet with the cut line on top (see Figure G).

Step 2: Shake the packet gently to settle the pellets to the bottom of the packet (see Figure H).

Figure G

Figure H

Step 3: Cut the packet along the cut line with scissors (see Figure I), or fold the packet back at the tear line (see Figure J) and tear open (see Figure K).

Figure I

Figure J

Figure K

Step 4: Pour the entire contents of the SOVALDI oral pellets packet directly in the mouth and swallow without chewing to avoid a bitter taste (see Figure L). Water may be taken after swallowing the pellets, if needed. Make sure that no SOVALDI oral pellets remain in the packet. If your healthcare provider prescribed more than one SOVALDI oral pellets packet, repeat Steps 1 through 4.

Figure L

Storing SOVALDI oral pellets

- Store SOVALDI pellets below 86°F (30°C).
  - Keep SOVALDI oral pellets and all medicines out of the reach of children.

Disposing of SOVALDI oral pellets

- Throw away any unused portion. Do not store and reuse any leftover SOVALDI mixture (pellets mixed with food).

For more information, call 1-800-445-3235 or go to www.SOVALDI.com.

Manufactured for and distributed by: Gilead Sciences, Inc., Foster City, CA 94404
SOVALDI is a trademark of Gilead Sciences, Inc., or its related companies.

© 2024 Gilead Sciences, Inc. All rights reserved.
204671-GS-011

This Instructions for Use has been approved by the U.S. Food and Drug Administration.
Issued: March 2020

PRINCIPAL DISPLAY PANEL - 400 mg Tablet Bottle Label

NDC 61958-1501-1
28 tablets

Sovaldi®
(sofosbuvir) tablets
400 mg

Take 1 tablet once daily

Note to pharmacist:
Do not cover ALERT box with pharmacy label.

ALERT: Find out about medicines that
should NOT be taken with Sovaldi

PRINCIPAL DISPLAY PANEL - 200 mg Tablet Bottle Label

NDC 61958-1503-1
28 tablets

Sovaldi®
(sofosbuvir) tablets

200 mg

Take 1 tablet once daily

Note to pharmacist:
Do not cover ALERT box with pharmacy label.

ALERT: Find out about medicines that
should NOT be taken with Sovaldi

PRINCIPAL DISPLAY PANEL - 150 mg Pellet Packet Carton Label

NDC 61958-1504-1
28 packets

Sovaldi®
(sofosbuvir) oral pellets

150 mg per packet

Rx only

Note to pharmacist: Do not cover ALERT box with pharmacy label.

ALERT: Find out about medicines that should NOT be taken with Sovaldi

PRINCIPAL DISPLAY PANEL - 200 mg Pellet Packet Carton Label

NDC 61958-1505-1
28 packets

Sovaldi®
(sofosbuvir) oral pellets

200 mg per packet

Rx only

Note to pharmacist: Do not cover ALERT box with pharmacy label.

ALERT: Find out about medicines that should NOT be taken with Sovaldi